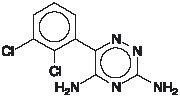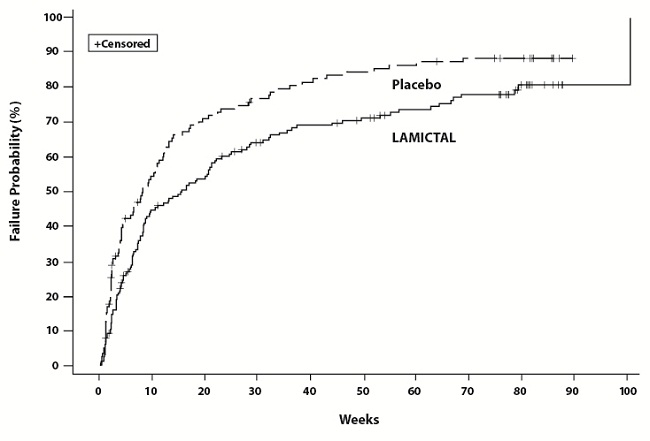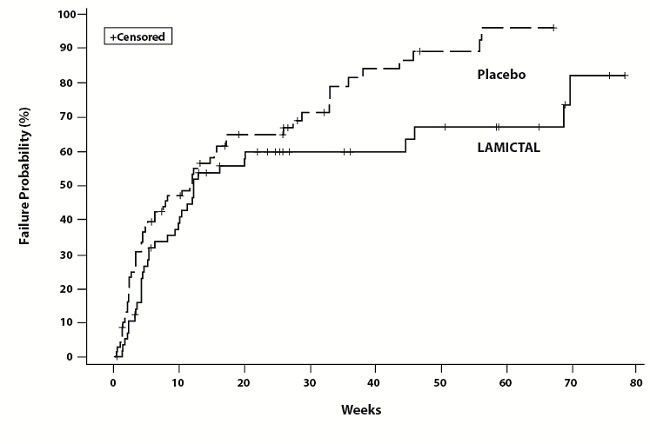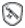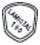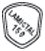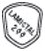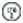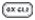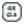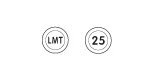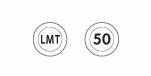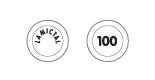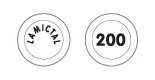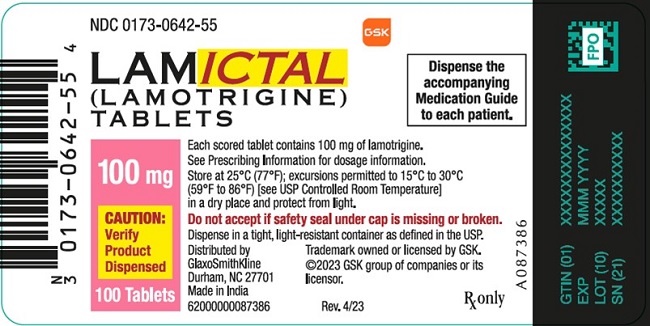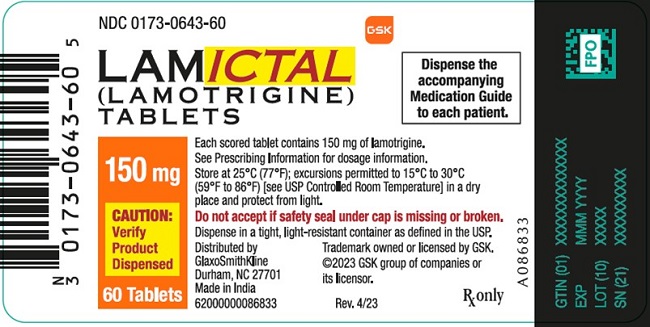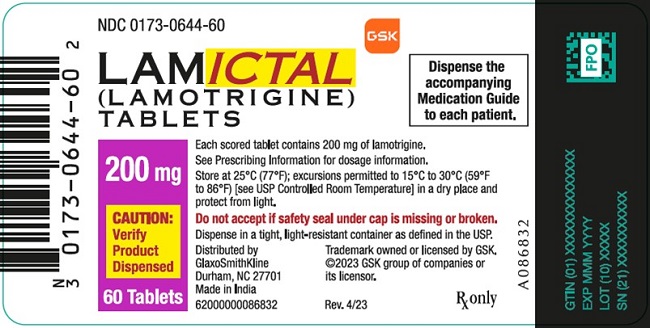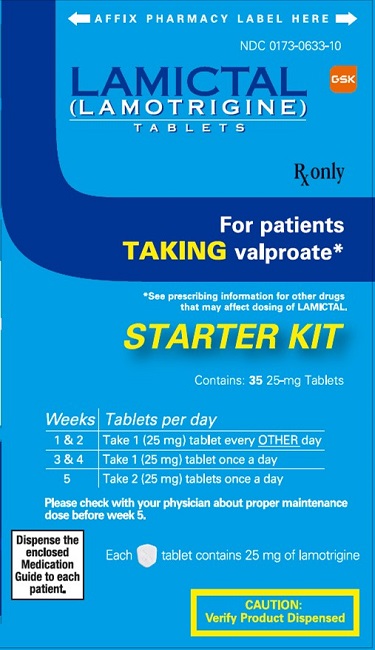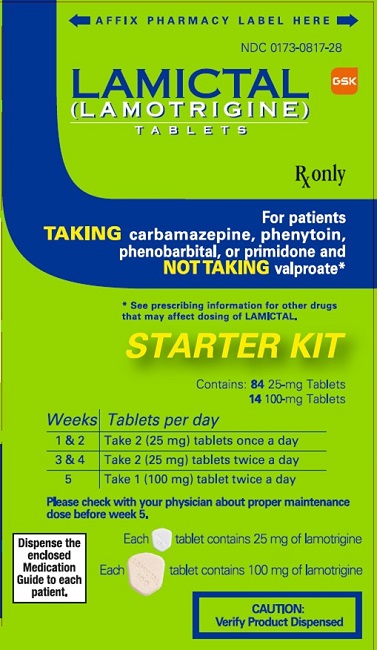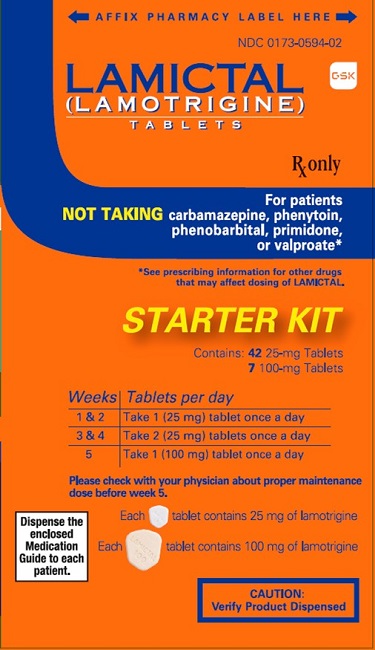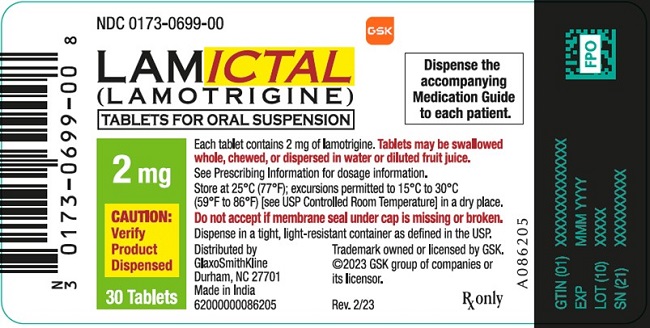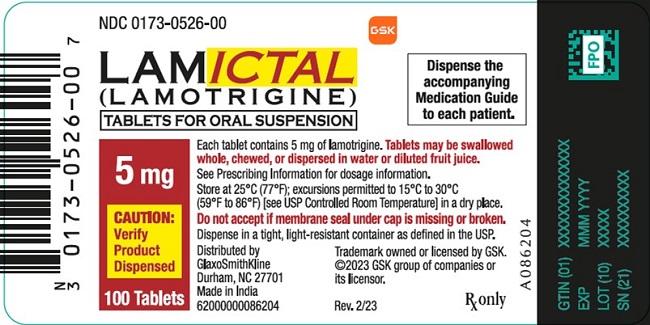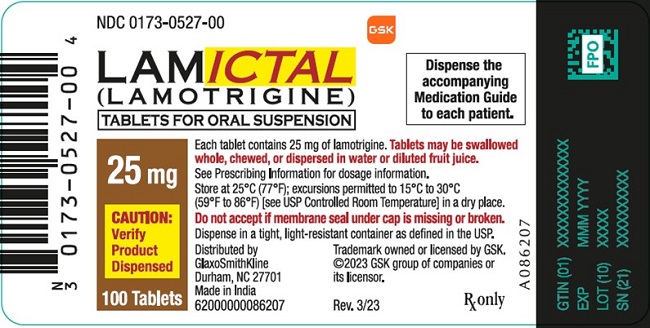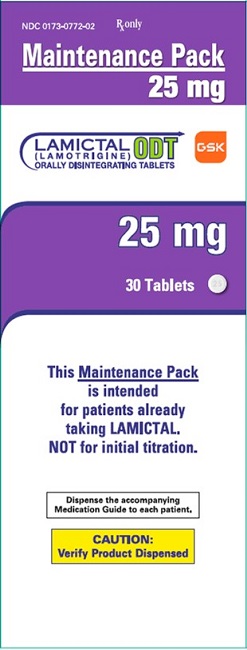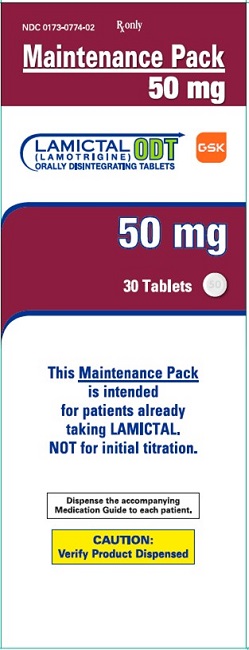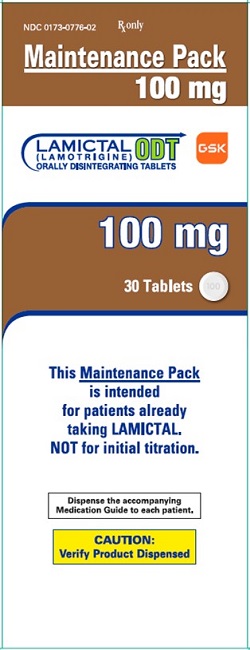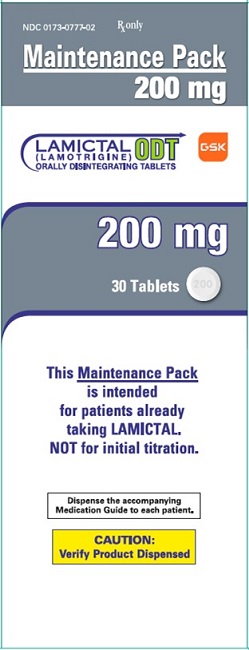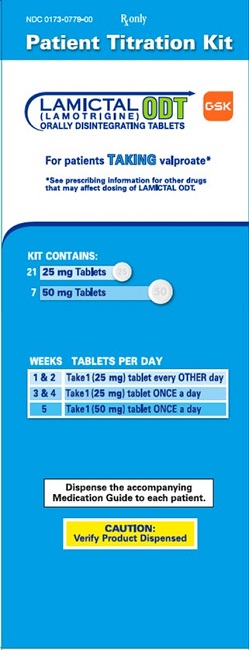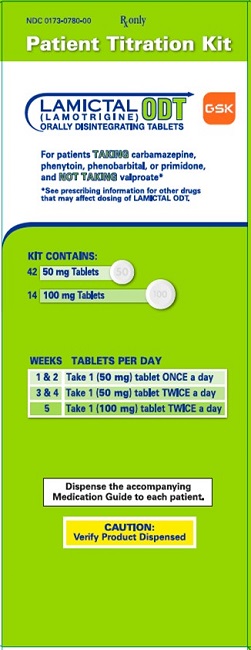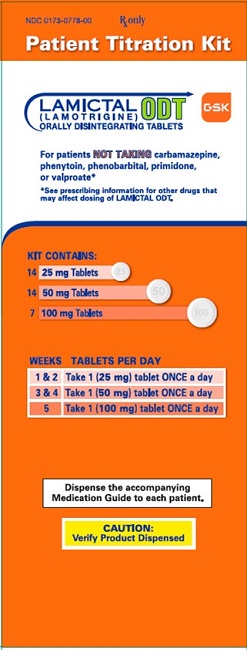 DRUG LABEL: LAMICTAL
NDC: 0173-0633 | Form: TABLET
Manufacturer: GlaxoSmithKline LLC
Category: prescription | Type: HUMAN PRESCRIPTION DRUG LABEL
Date: 20251010

ACTIVE INGREDIENTS: LAMOTRIGINE 25 mg/1 1
INACTIVE INGREDIENTS: LACTOSE, UNSPECIFIED FORM; MAGNESIUM STEARATE; MICROCRYSTALLINE CELLULOSE; POVIDONE, UNSPECIFIED; SODIUM STARCH GLYCOLATE TYPE A POTATO

HIGHLIGHTS OF PRESCRIBING INFORMATION

These highlights do not include all the information needed to use LAMICTAL safely and effectively. See full prescribing information for LAMICTAL.
LAMICTAL (lamotrigine) tablets, for oral use
LAMICTAL (lamotrigine) tablets for oral suspension
LAMICTAL ODT (lamotrigine) orally disintegrating tablets, for oral use
Initial U.S. Approval: 1994

RECENT MAJOR CHANGES

Boxed Warning | 10/2025
Dosage and Administration (2.1, 2.2, 2.4) | 4/2025
Warnings and Precautions, Serious Skin Rashes (5.1) Concomitant Use with Estrogen-Containing Products, Including Oral Contraceptives (5.9) Sudden Unexplained Death in Epilepsy (5.12) – removal | 10/2025 4/2025 4/2025

WARNING: SERIOUS SKIN RASHES

See full prescribing information for complete boxed warning.

- Cases of life-threatening serious rashes, including Stevens-Johnson syndrome and toxic epidermal necrolysis, and/or rash-related death have been caused by lamotrigine. The rate of serious rash is greater in pediatric patients than in adults. Additional factors that may increase the risk of rash include:
  - coadministration with valproate.
  - exceeding recommended initial dose of LAMICTAL.
  - exceeding recommended dose escalation for LAMICTAL.
  - presence of the HLA-B*1502 allele. (5.1)
- Benign rashes are also caused by lamotrigine; however, it is not possible to predict which rashes will prove to be serious or life threatening. LAMICTAL should be discontinued at the first sign of rash, unless the rash is clearly not drug related. (5.1)

1 INDICATIONS AND USAGE

LAMICTAL is indicated for:

Epilepsy—adjunctive therapy in patients aged 2 years and older:

- partial-onset seizures.
- primary generalized tonic-clonic (PGTC) seizures.
- generalized seizures of Lennox-Gastaut syndrome. (1.1)

Epilepsy—monotherapy in patients aged 16 years and older: Conversion to monotherapy in patients with partial-onset seizures who are receiving treatment with carbamazepine, phenytoin, phenobarbital, primidone, or valproate as the single antiepileptic drug. (1.1)

Bipolar disorder: Maintenance treatment of bipolar I disorder to delay the time to occurrence of mood episodes in patients treated for acute mood episodes with standard therapy. (1.2)

Limitations of Use: Treatment of acute manic or mixed episodes is not recommended. Effectiveness of LAMICTAL in the acute treatment of mood episodes has not been established.

2 DOSAGE AND ADMINISTRATION

- Dosing is based on concomitant medications, indication, and patient age. (2.1, 2.2, 2.3, 2.4)
- To avoid an increased risk of rash, the recommended initial dose and subsequent dose escalations should not be exceeded. LAMICTAL Starter Kits and LAMICTAL ODT Patient Titration Kits are available for the first 5 weeks of treatment. (2.1, 16)
- Do not restart LAMICTAL in patients who discontinued due to rash unless the potential benefits clearly outweigh the risks. (2.1, 5.1)
- Adjustments to maintenance doses will be necessary in most patients starting or stopping estrogen-containing products, including oral contraceptives. (2.1, 5.9)
- Discontinuation: Taper over a period of at least 2 weeks (approximately 50% dose reduction per week). (2.1, 5.10)

Epilepsy:

- Adjunctive therapy—See Table 1 for patients older than 12 years and Tables 2 and 3 for patients aged 2 to 12 years. (2.2)
- Conversion to monotherapy—See Table 4. (2.3)

Bipolar disorder: See Tables 5 and 6. (2.4)

3 DOSAGE FORMS AND STRENGTHS

- Tablets: 25 mg, 100 mg, 150 mg, and 200 mg; scored. (3.1, 16)
- Tablets for oral suspension: 2 mg, 5 mg, and 25 mg. (3.2, 16)
- Orally disintegrating tablets: 25 mg, 50 mg, 100 mg, and 200 mg. (3.3, 16)

4 CONTRAINDICATIONS

Hypersensitivity to the drug or its ingredients. (Boxed Warning, 4)

5 WARNINGS AND PRECAUTIONS

- Life-threatening serious rash and/or rash-related death: Discontinue at the first sign of rash, unless the rash is clearly not drug related. (Boxed Warning, 5.1)
- Hemophagocytic lymphohistiocytosis: Consider this diagnosis and evaluate patients immediately if they develop signs or symptoms of systemic inflammation. Discontinue LAMICTAL if an alternative etiology is not established. (5.2)
- Fatal or life-threatening hypersensitivity reaction: Multiorgan hypersensitivity reactions, also known as drug reaction with eosinophilia and systemic symptoms, may be fatal or life threatening. Early signs may include rash, fever, and lymphadenopathy. These reactions may be associated with other organ involvement, such as hepatitis, hepatic failure, blood dyscrasias, or acute multiorgan failure. LAMICTAL should be discontinued if alternate etiology for this reaction is not found. (5.3)
- Cardiac rhythm and conduction abnormalities: Based on in vitro findings, LAMICTAL could cause serious arrhythmias and/or death in patients with certain underlying cardiac disorders or arrhythmias. Any expected or observed benefit of LAMICTAL in an individual patient with clinically important structural or functional heart disease must be carefully weighed against the risk for serious arrythmias and/or death for that patient. (5.4)
- Blood dyscrasias (e.g., neutropenia, thrombocytopenia, pancytopenia): May occur, either with or without an associated hypersensitivity syndrome. Monitor for signs of anemia, unexpected infection, or bleeding. (5.5)
- Suicidal behavior and ideation: Monitor for suicidal thoughts or behaviors. (5.6)
- Aseptic meningitis: Monitor for signs of meningitis. (5.7)
- Medication errors due to product name confusion: Strongly advise patients to visually inspect tablets to verify the received drug is correct. (5.8, 16, 17)

6 ADVERSE REACTIONS

Epilepsy: Most common adverse reactions (incidence ≥10%) in adults were dizziness, headache, diplopia, ataxia, nausea, blurred vision, somnolence, rhinitis, pharyngitis, and rash. Additional adverse reactions (incidence ≥10%) reported in children included vomiting, infection, fever, accidental injury, diarrhea, abdominal pain, and tremor. (6.1)

Bipolar disorder: Most common adverse reactions (incidence >5%) in adults were nausea, insomnia, somnolence, back pain, fatigue, rash, rhinitis, abdominal pain, and xerostomia. (6.1)

To report SUSPECTED ADVERSE REACTIONS, contact GlaxoSmithKline at 1-888-825-5249 or FDA at 1-800-FDA-1088 or www.fda.gov/medwatch.

7 DRUG INTERACTIONS

- Valproate increases lamotrigine concentrations more than 2-fold. (7, 12.3)
- Carbamazepine, phenytoin, phenobarbital, primidone, and rifampin decrease lamotrigine concentrations by approximately 40%. (7, 12.3)
- Estrogen-containing oral contraceptives decrease lamotrigine concentrations by approximately 50%. (7, 12.3)
- Protease inhibitors lopinavir/ritonavir and atazanavir/lopinavir decrease lamotrigine exposure by approximately 50% and 32%, respectively. (7, 12.3)
- Coadministration with organic cationic transporter 2 substrates with narrow therapeutic index is not recommended (7, 12.3)

8 USE IN SPECIFIC POPULATIONS

- Pregnancy: Based on animal data may cause fetal harm. (8.1)
- Hepatic impairment: Dosage adjustments required in patients with moderate and severe liver impairment. (2.1, 8.6)
- Renal impairment: Reduced maintenance doses may be effective for patients with significant renal impairment. (2.1, 8.7)

FULL PRESCRIBING INFORMATION

WARNING: SERIOUS SKIN RASHES

LAMICTAL can cause serious rashes requiring hospitalization and discontinuation of treatment. The incidence of these rashes, which have included Stevens-Johnson syndrome, is approximately 0.3% to 0.8% in pediatric patients (aged 2 to 17 years) and 0.08% to 0.3% in adults receiving LAMICTAL. One rash-related death was reported in a prospectively followed cohort of 1,983 pediatric patients (aged 2 to 16 years) with epilepsy taking LAMICTAL as adjunctive therapy. In worldwide postmarketing experience, rare cases of toxic epidermal necrolysis and/or rash-related death have been reported in adult and pediatric patients, but their numbers are too few to permit a precise estimate of the rate.

In addition to age, factors that may increase the risk of occurrence or the severity of rash caused by LAMICTAL include (1) coadministration of LAMICTAL with valproate (includes valproic acid and divalproex sodium), (2) exceeding the recommended initial dose of LAMICTAL, (3) exceeding the recommended dose escalation for LAMICTAL, or (4) the presence of the HLA-B*1502 allele. However, cases have occurred in the absence of these factors.

Nearly all cases of life-threatening rashes caused by LAMICTAL have occurred within 2 to 8 weeks of treatment initiation. However, isolated cases have occurred after prolonged treatment (e.g., 6 months). Accordingly, duration of therapy cannot be relied upon as means to predict the potential risk heralded by the first appearance of a rash.

Although benign rashes are also caused by LAMICTAL, it is not possible to predict reliably which rashes will prove to be serious or life threatening. Accordingly, LAMICTAL should ordinarily be discontinued at the first sign of rash, unless the rash is clearly not drug related. Discontinuation of treatment may not prevent a rash from becoming life threatening or permanently disabling or disfiguring [see Warnings and Precautions (5.1)].

1 INDICATIONS AND USAGE

1.1 Epilepsy

Adjunctive Therapy

LAMICTAL is indicated as adjunctive therapy for the following seizure types in patients aged 2 years and older:

- partial-onset seizures.
- primary generalized tonic-clonic (PGTC) seizures.
- generalized seizures of Lennox-Gastaut syndrome.

Monotherapy

LAMICTAL is indicated for conversion to monotherapy in adults (aged 16 years and older) with partial-onset seizures who are receiving treatment with carbamazepine, phenytoin, phenobarbital, primidone, or valproate as the single antiepileptic drug (AED).

Safety and effectiveness of LAMICTAL have not been established (1) as initial monotherapy; (2) for conversion to monotherapy from AEDs other than carbamazepine, phenytoin, phenobarbital, primidone, or valproate; or (3) for simultaneous conversion to monotherapy from 2 or more concomitant AEDs.

1.2 Bipolar Disorder

LAMICTAL is indicated for the maintenance treatment of bipolar I disorder to delay the time to occurrence of mood episodes (depression, mania, hypomania, mixed episodes) in patients treated for acute mood episodes with standard therapy [see Clinical Studies (14.2)].

Limitations of Use

Treatment of acute manic or mixed episodes is not recommended. Effectiveness of LAMICTAL in the acute treatment of mood episodes has not been established.

2 DOSAGE AND ADMINISTRATION

2.1 General Dosing Considerations

Rash

There are suggestions that the risk of severe, potentially life-threatening rash may be increased by (1) coadministration of LAMICTAL with valproate, (2) exceeding the recommended initial dose of LAMICTAL, or (3) exceeding the recommended dose escalation for LAMICTAL. However, cases have occurred in the absence of these factors [see Boxed Warning]. Therefore, it is important that the dosing recommendations be followed closely.

The risk of nonserious rash may be increased when the recommended initial dose and/or the rate of dose escalation for LAMICTAL is exceeded and in patients with a history of allergy or rash to other AEDs.

LAMICTAL Starter Kits and LAMICTAL ODT Patient Titration Kits provide LAMICTAL at doses consistent with the recommended titration schedule for the first 5 weeks of treatment, based upon concomitant medications, for patients with epilepsy (older than 12 years) and bipolar I disorder (adults) and are intended to help reduce the potential for rash. The use of LAMICTAL Starter Kits and LAMICTAL ODT Patient Titration Kits is recommended for appropriate patients who are starting or restarting LAMICTAL [see How Supplied/Storage and Handling (16)].

It is recommended that LAMICTAL not be restarted in patients who discontinued due to rash associated with prior treatment with lamotrigine unless the potential benefits clearly outweigh the risks. If the decision is made to restart a patient who has discontinued LAMICTAL, the need to restart with the initial dosing recommendations should be assessed. The greater the interval of time since the previous dose, the greater consideration should be given to restarting with the initial dosing recommendations. If a patient has discontinued lamotrigine for a period of more than 5 half-lives, it is recommended that initial dosing recommendations and guidelines be followed. The half-life of lamotrigine is affected by other concomitant medications [see Clinical Pharmacology (12.3)].

LAMICTAL Added to Drugs Known to Induce or Inhibit Glucuronidation

Because lamotrigine is metabolized predominantly by glucuronic acid conjugation, drugs that are known to induce or inhibit glucuronidation may affect the apparent clearance of lamotrigine. Drugs that induce glucuronidation include carbamazepine, phenytoin, phenobarbital, primidone, rifampin, estrogen-containing products, including oral contraceptives, and the protease inhibitors lopinavir/ritonavir and atazanavir/ritonavir. Valproate inhibits glucuronidation. For dosing considerations for LAMICTAL in patients on estrogen-containing products, including contraceptives, and atazanavir/ritonavir, see below and Table 13. For dosing considerations for LAMICTAL in patients on other drugs known to induce or inhibit glucuronidation, see Tables 1, 2, 5-6, and 13.

Target Plasma Levels for Patients with Epilepsy or Bipolar Disorder

A therapeutic plasma concentration range has not been established for lamotrigine. Dosing of LAMICTAL should be based on therapeutic response [see Clinical Pharmacology (12.3)].

Women Taking Estrogen-Containing Oral Contraceptives

Starting LAMICTAL in Women Taking Estrogen-Containing Oral Contraceptives: Although estrogen-containing oral contraceptives have been shown to increase the clearance of lamotrigine, no adjustments to the recommended dose-escalation guidelines for LAMICTAL should be necessary solely based on the use of estrogen-containing oral contraceptives [see Clinical Pharmacology (12.3)]. Therefore, dose escalation should follow the recommended guidelines for initiating adjunctive therapy with LAMICTAL based on the concomitant AED or other concomitant medications (see Tables 1, 5, and 7). See below for adjustments to maintenance doses of LAMICTAL in women taking estrogen-containing oral contraceptives.

Adjustments to the Maintenance Dose of LAMICTAL in Women Taking Estrogen-Containing Oral Contraceptives:

(1) Taking Estrogen-Containing Oral Contraceptives: In women not taking carbamazepine, phenytoin, phenobarbital, primidone, or other drugs such as rifampin and the protease inhibitors lopinavir/ritonavir and atazanavir/ritonavir that induce lamotrigine glucuronidation, the maintenance dose of LAMICTAL will in most cases need to be increased by as much as 2-fold over the recommended target maintenance dose to maintain a consistent lamotrigine plasma level [see Drug Interactions (7), Clinical Pharmacology (12.3)].

(2) Starting Estrogen-Containing Oral Contraceptives: In women taking a stable dose of LAMICTAL and not taking carbamazepine, phenytoin, phenobarbital, primidone, or other drugs such as rifampin and the protease inhibitors lopinavir/ritonavir and atazanavir/ritonavir that induce lamotrigine glucuronidation, the maintenance dose will in most cases need to be increased by as much as 2-fold to maintain a consistent lamotrigine plasma level [see Drug Interactions (7), Clinical Pharmacology (12.3)]. The dose increases should begin at the same time that the oral contraceptive is introduced and continue, based on clinical response, no more rapidly than 50 to 100 mg/day every week. Dose increases should not exceed the recommended rate (see Tables 1 and 5) unless lamotrigine plasma levels or clinical response support larger increases. Gradual transient increases in lamotrigine plasma levels may occur during the week of inactive hormonal preparation (pill-free week), and these increases will be greater if dose increases are made in the days before or during the week of inactive hormonal preparation. Increased lamotrigine plasma levels could result in additional adverse reactions, such as dizziness, ataxia, and diplopia. If adverse reactions attributable to LAMICTAL consistently occur during the pill-free week, dose adjustments to the overall maintenance dose may be necessary. Dose adjustments limited to the pill-free week are not recommended. For women taking LAMICTAL in addition to carbamazepine, phenytoin, phenobarbital, primidone, or other drugs such as rifampin and the protease inhibitors lopinavir/ritonavir and atazanavir/ritonavir that induce lamotrigine glucuronidation, no adjustment to the dose of LAMICTAL should be necessary [see Drug Interactions (7), Clinical Pharmacology (12.3)].

(3) Stopping Estrogen-Containing Oral Contraceptives: In women not taking carbamazepine, phenytoin, phenobarbital, primidone, or other drugs such as rifampin and the protease inhibitors lopinavir/ritonavir and atazanavir/ritonavir that induce lamotrigine glucuronidation, the maintenance dose of LAMICTAL will in most cases need to be decreased by as much as 50% in order to maintain a consistent lamotrigine plasma level [see Drug Interactions (7), Clinical Pharmacology (12.3)]. The decrease in dose of LAMICTAL should not exceed 25% of the total daily dose per week over a 2-week period, unless clinical response or lamotrigine plasma levels indicate otherwise [see Clinical Pharmacology (12.3)]. In women taking LAMICTAL in addition to carbamazepine, phenytoin, phenobarbital, primidone, or other drugs such as rifampin and the protease inhibitors lopinavir/ritonavir and atazanavir/ritonavir that induce lamotrigine glucuronidation, no adjustment to the dose of LAMICTAL should be necessary [see Drug Interactions (7), Clinical Pharmacology (12.3)].

Women and Other Hormonal Contraceptive Preparations or Hormone Replacement Therapy

The effect of other hormonal contraceptive preparations or hormone replacement therapy (HRT) on the pharmacokinetics of lamotrigine has not been systematically evaluated. Other estrogen-containing therapies, such as HRT, may interfere with lamotrigine. Therefore, close clinical monitoring on effectiveness of LAMICTAL with dose adjustment may be necessary [see Warnings and Precautions (5.9)]. It has been reported that ethinylestradiol, not progestogens, increased the clearance of lamotrigine up to 2-fold, and the progestin-only pills had no effect on lamotrigine plasma levels. Therefore, adjustments to the dosage of LAMICTAL in the presence of progestogens alone will likely not be needed.

Patients Taking Atazanavir/Ritonavir

While atazanavir/ritonavir does reduce the lamotrigine plasma concentration, no adjustments to the recommended dose-escalation guidelines for LAMICTAL should be necessary solely based on the use of atazanavir/ritonavir. Dose escalation should follow the recommended guidelines for initiating adjunctive therapy with LAMICTAL based on concomitant AED or other concomitant medications (see Tables 1, 2, and 5). In patients already taking maintenance doses of LAMICTAL and not taking glucuronidation inducers, the dose of LAMICTAL may need to be increased if atazanavir/ritonavir is added or decreased if atazanavir/ritonavir is discontinued [see Clinical Pharmacology (12.3)].

Patients with Hepatic Impairment

Experience in patients with hepatic impairment is limited. Based on a clinical pharmacology study in 24 subjects with mild, moderate, and severe liver impairment, the following general recommendations can be made [see Use in Specific Populations (8.6), Clinical Pharmacology (12.3)]. No dosage adjustment is needed in patients with mild liver impairment. Initial, escalation, and maintenance doses should generally be reduced by approximately 25% in patients with moderate and severe liver impairment without ascites and 50% in patients with severe liver impairment with ascites. Escalation and maintenance doses may be adjusted according to clinical response.

Patients with Renal Impairment

Initial doses of LAMICTAL should be based on patients’ concomitant medications (see Tables 1-3 and 5); reduced maintenance doses may be effective for patients with significant renal impairment [see Use in Specific Populations (8.7), Clinical Pharmacology (12.3)]. Few patients with severe renal impairment have been evaluated during chronic treatment with LAMICTAL. Because there is inadequate experience in this population, LAMICTAL should be used with caution in these patients.

Discontinuation Strategy

Epilepsy: For patients receiving LAMICTAL in combination with other AEDs, a re-evaluation of all AEDs in the regimen should be considered if a change in seizure control or an appearance or worsening of adverse reactions is observed.

If a decision is made to discontinue therapy with LAMICTAL, a step-wise reduction of dose over at least 2 weeks (approximately 50% per week) is recommended unless safety concerns require a more rapid withdrawal [see Warnings and Precautions (5.10)].

Discontinuing carbamazepine, phenytoin, phenobarbital, primidone, or other drugs such as rifampin and the protease inhibitors lopinavir/ritonavir and atazanavir/ritonavir that induce lamotrigine glucuronidation should prolong the half-life of lamotrigine; discontinuing valproate should shorten the half-life of lamotrigine.

Bipolar Disorder: In the controlled clinical trials, there was no increase in the incidence, type, or severity of adverse reactions following abrupt termination of LAMICTAL. In the clinical development program in adults with bipolar disorder, 2 patients experienced seizures shortly after abrupt withdrawal of LAMICTAL. Discontinuation of LAMICTAL should involve a step-wise reduction of dose over at least 2 weeks (approximately 50% per week) unless safety concerns require a more rapid withdrawal [see Warnings and Precautions (5.10)].

2.2 Epilepsy—Adjunctive Therapy

This section provides specific dosing recommendations for patients older than 12 years and patients aged 2 to 12 years. Within each of these age-groups, specific dosing recommendations are provided depending upon concomitant AEDs or other concomitant medications (see Table 1 for patients older than 12 years and Table 2 for patients aged 2 to 12 years). A weight-based dosing guide for patients aged 2 to 12 years on concomitant valproate is provided in Table 3.

Patients Older than 12 Years

Recommended dosing guidelines are summarized in Table 1.

Table 1. Escalation Regimen for LAMICTAL in Patients Older than 12 Years with Epilepsy
 | In Patients TAKING Valproatea | In Patients NOT TAKING Carbamazepine, Phenytoin, Phenobarbital, Primidone,b or Valproatea | In Patients TAKING Carbamazepine, Phenytoin, Phenobarbital, or Primidoneb and NOT TAKING Valproatea
Weeks 1 and 2 | 25 mg every other day | 25 mg every day | 50 mg/day
Weeks 3 and 4 | 25 mg every day | 50 mg/day | 100 mg/day (in 2 divided doses)
Week 5 onward to maintenance | Increase by 25 to 50 mg/day every 1 to 2 weeks. | Increase by 50 mg/day every 1 to 2 weeks. | Increase by 100 mg/day every 1 to 2 weeks.
Usual maintenance dose | 100 to 200 mg/day with valproate alone; 100 to 400 mg/day with valproate and other drugs that induce glucuronidation; (in 1 or 2 divided doses) | 225 to 375 mg/day (in 2 divided doses) | 300 to 500 mg/day (in 2 divided doses)
a Valproate has been shown to inhibit glucuronidation and decrease the apparent clearance of lamotrigine [see Drug Interactions (7), Clinical Pharmacology (12.3)].
b Drugs that induce lamotrigine glucuronidation and increase clearance, other than the specified AEDs, include estrogen-containing oral contraceptives, rifampin, and the protease inhibitors lopinavir/ritonavir and atazanavir/ritonavir. Dosing recommendations for estrogen-containing products, including oral contraceptives, and the protease inhibitor atazanavir/ritonavir can be found in General Dosing Considerations [see Dosage and Administration (2.1)]. Patients on rifampin and the protease inhibitor lopinavir/ritonavir should follow the same dosing titration/maintenance regimen used with AEDs that induce glucuronidation and increase clearance [see Dosage and Administration (2.1), Drug Interactions (7), Clinical Pharmacology (12.3)].

Patients Aged 2 to 12 Years

Recommended dosing guidelines are summarized in Table 2.

Lower starting doses and slower dose escalations than those used in clinical trials are recommended because of the suggestion that the risk of rash may be decreased by lower starting doses and slower dose escalations. Therefore, maintenance doses will take longer to reach in clinical practice than in clinical trials. It may take several weeks to months to achieve an individualized maintenance dose. Maintenance doses in patients weighing <30 kg, regardless of age or concomitant AED, may need to be increased as much as 50%, based on clinical response.

The smallest available strength of LAMICTAL tablets for oral suspension is 2 mg, and only whole tablets should be administered. If the calculated dose cannot be achieved using whole tablets, the dose should be rounded down to the nearest whole tablet [see How Supplied/Storage and Handling (16), Medication Guide].

Table 2. Escalation Regimen for LAMICTAL in Patients Aged 2 to 12 Years with Epilepsy
 | In Patients TAKING Valproatea | In Patients NOT TAKING Carbamazepine, Phenytoin, Phenobarbital, Primidone,b or Valproatea | In Patients TAKING Carbamazepine, Phenytoin, Phenobarbital, or Primidoneb and NOT TAKING Valproatea
Weeks 1 and 2 | 0.15 mg/kg/day in 1 or 2 divided doses, rounded down to the nearest whole tablet (see Table 3 for weight-based dosing guide) | 0.3 mg/kg/day in 1 or 2 divided doses, rounded down to the nearest whole tablet | 0.6 mg/kg/day in 2 divided doses, rounded down to the nearest whole tablet
Weeks 3 and 4 | 0.3 mg/kg/day in 1 or 2 divided doses, rounded down to the nearest whole tablet (see Table 3 for weight-based dosing guide) | 0.6 mg/kg/day in 2 divided doses, rounded down to the nearest whole tablet | 1.2 mg/kg/day in 2 divided doses, rounded down to the nearest whole tablet
Week 5 onward to maintenance | The dose should be increased every 1 to 2 weeks as follows: calculate 0.3 mg/kg/day, round this amount down to the nearest whole tablet, and add this amount to the previously administered daily dose. | The dose should be increased every 1 to 2 weeks as follows: calculate 0.6 mg/kg/day, round this amount down to the nearest whole tablet, and add this amount to the previously administered daily dose. | The dose should be increased every 1 to 2 weeks as follows: calculate 1.2 mg/kg/day, round this amount down to the nearest whole tablet, and add this amount to the previously administered daily dose.
Usual maintenance dose | 1 to 5 mg/kg/day (maximum 200 mg/day in 1 or 2 divided doses); 1 to 3 mg/kg/day with valproate alone | 4.5 to 7.5 mg/kg/day (maximum 300 mg/day in 2 divided doses) | 5 to 15 mg/kg/day (maximum 400 mg/day in 2 divided doses)
Maintenance dose in patients <30 kg | May need to be increased by as much as 50%, based on clinical response. | May need to be increased by as much as 50%, based on clinical response. | May need to be increased by as much as 50%, based on clinical response.
Note: Only whole tablets should be used for dosing.
a Valproate has been shown to inhibit glucuronidation and decrease the apparent clearance of lamotrigine [see Drug Interactions (7), Clinical Pharmacology (12.3)].
b Drugs that induce lamotrigine glucuronidation and increase clearance, other than the specified AEDs, include estrogen-containing oral contraceptives, rifampin, and the protease inhibitors lopinavir/ritonavir and atazanavir/ritonavir. Dosing recommendations for estrogen-containing products, including oral contraceptives, and the protease inhibitor atazanavir/ritonavir, can be found in General Dosing Considerations [see Dosage and Administration (2.1)]. Patients on rifampin and the protease inhibitor lopinavir/ritonavir should follow the same dosing titration/maintenance regimen used with AEDs that induce glucuronidation and increase clearance [see Dosage and Administration (2.1), Drug Interactions (7), Clinical Pharmacology (12.3)].

Table 3. The Initial Weight-Based Dosing Guide for Patients Aged 2 to 12 Years Taking Valproate (Weeks 1 to 4) with Epilepsy
If the patient’s weight is |  | Give this daily dose, using the most appropriate combination of LAMICTAL 2- and 5-mg tablets
Greater than | And less than | Weeks 1 and 2 | Weeks 3 and 4
6.7 kg | 14 kg | 2 mg every other day | 2 mg every day
14.1 kg | 27 kg | 2 mg every day | 4 mg every day
27.1 kg | 34 kg | 4 mg every day | 8 mg every day
34.1 kg | 40 kg | 5 mg every day | 10 mg every day

Usual Adjunctive Maintenance Dose for Epilepsy

The usual maintenance doses identified in Tables 1 and 2 are derived from dosing regimens employed in the placebo-controlled adjunctive trials in which the efficacy of LAMICTAL was established. In patients receiving multidrug regimens employing carbamazepine, phenytoin, phenobarbital, or primidone without valproate, maintenance doses of adjunctive LAMICTAL as high as 700 mg/day have been used. In patients receiving valproate alone, maintenance doses of adjunctive LAMICTAL as high as 200 mg/day have been used. The advantage of using doses above those recommended in Tables 1-4 has not been established in controlled trials.

2.3 Epilepsy—Conversion from Adjunctive Therapy to Monotherapy

The goal of the transition regimen is to attempt to maintain seizure control while mitigating the risk of serious rash associated with the rapid titration of LAMICTAL.

The recommended maintenance dose of LAMICTAL as monotherapy is 500 mg/day given in 2 divided doses.

To avoid an increased risk of rash, the recommended initial dose and subsequent dose escalations for LAMICTAL should not be exceeded [see Boxed Warning].

Conversion from Adjunctive Therapy with Carbamazepine, Phenytoin, Phenobarbital, or Primidone to Monotherapy with LAMICTAL

After achieving a dose of 500 mg/day of LAMICTAL using the guidelines in Table 1, the concomitant enzyme-inducing AED should be withdrawn by 20% decrements each week over a 4-week period. The regimen for the withdrawal of the concomitant AED is based on experience gained in the controlled monotherapy clinical trial.

Conversion from Adjunctive Therapy with Valproate to Monotherapy with LAMICTAL

The conversion regimen involves the 4 steps outlined in Table 4.

Table 4. Conversion from Adjunctive Therapy with Valproate to Monotherapy with LAMICTAL in Patients Aged 16 Years and Older with Epilepsy
 | LAMICTAL | Valproate
Step 1 | Achieve a dose of 200 mg/day according to guidelines in Table 1. | Maintain established stable dose.
Step 2 | Maintain at 200 mg/day. | Decrease dose by decrements no greater than 500 mg/day/week to 500 mg/day and then maintain for 1 week.
Step 3 | Increase to 300 mg/day and maintain for 1 week. | Simultaneously decrease to 250 mg/day and maintain for 1 week.
Step 4 | Increase by 100 mg/day every week to achieve maintenance dose of 500 mg/day. | Discontinue.

Conversion from Adjunctive Therapy with Antiepileptic Drugs other than Carbamazepine, Phenytoin, Phenobarbital, Primidone, or Valproate to Monotherapy with LAMICTAL

No specific dosing guidelines can be provided for conversion to monotherapy with LAMICTAL with AEDs other than carbamazepine, phenytoin, phenobarbital, primidone, or valproate.

2.4 Bipolar Disorder

The goal of maintenance treatment with LAMICTAL is to delay the time to occurrence of mood episodes (depression, mania, hypomania, mixed episodes) in patients treated for acute mood episodes with standard therapy [see Indications and Usage (1.2)].

Patients taking LAMICTAL for more than 16 weeks should be periodically reassessed to determine the need for maintenance treatment.

Adults

The target dose of LAMICTAL is 200 mg/day (100 mg/day in patients taking valproate, which decreases the apparent clearance of lamotrigine, and 400 mg/day in patients not taking valproate and taking either carbamazepine, phenytoin, phenobarbital, primidone, or other drugs such as rifampin and the protease inhibitor lopinavir/ritonavir that increase the apparent clearance of lamotrigine). In the clinical trials, doses up to 400 mg/day as monotherapy were evaluated; however, no additional benefit was seen at 400 mg/day compared with 200 mg/day [see Clinical Studies (14.2)]. Accordingly, doses above 200 mg/day are not recommended.

Treatment with LAMICTAL is introduced, based on concurrent medications, according to the regimen outlined in Table 5. If other psychotropic medications are withdrawn following stabilization, the dose of LAMICTAL should be adjusted. In patients discontinuing valproate, the dose of LAMICTAL should be doubled over a 2-week period in equal weekly increments (see Table 6). In patients discontinuing carbamazepine, phenytoin, phenobarbital, primidone, or other drugs such as rifampin and the protease inhibitors lopinavir/ritonavir and atazanavir/ritonavir that induce lamotrigine glucuronidation, the dose of LAMICTAL should remain constant for the first week and then should be decreased by half over a 2-week period in equal weekly decrements (see Table 6). The dose of LAMICTAL may then be further adjusted to the target dose (200 mg) as clinically indicated.

If other drugs are subsequently introduced, the dose of LAMICTAL may need to be adjusted. In particular, the introduction of valproate requires reduction in the dose of LAMICTAL [see Drug Interactions (7), Clinical Pharmacology (12.3)].

To avoid an increased risk of rash, the recommended initial dose and subsequent dose escalations of LAMICTAL should not be exceeded [see Boxed Warning].

Table 5. Escalation Regimen for LAMICTAL in Adults with Bipolar Disorder
 | In Patients TAKING Valproatea | In Patients NOT TAKING Carbamazepine, Phenytoin, Phenobarbital, Primidone,b or Valproatea | In Patients TAKING Carbamazepine, Phenytoin, Phenobarbital, or Primidoneb and NOT TAKING Valproatea
Weeks 1 and 2 | 25 mg every other day | 25 mg daily | 50 mg daily
Weeks 3 and 4 | 25 mg daily | 50 mg daily | 100 mg daily, in divided doses
Week 5 | 50 mg daily | 100 mg daily | 200 mg daily, in divided doses
Week 6 | 100 mg daily | 200 mg daily | 300 mg daily, in divided doses
Week 7 | 100 mg daily | 200 mg daily | up to 400 mg daily, in divided doses
a Valproate has been shown to inhibit glucuronidation and decrease the apparent clearance of lamotrigine [see Drug Interactions (7), Clinical Pharmacology (12.3)].
b Drugs that induce lamotrigine glucuronidation and increase clearance, other than the specified AEDs, include estrogen-containing products, including oral contraceptives, rifampin, and the protease inhibitors lopinavir/ritonavir and atazanavir/ritonavir. Dosing recommendations for oral contraceptives and the protease inhibitor atazanavir/ritonavir can be found in General Dosing Considerations [see Dosage and Administration (2.1)]. Patients on rifampin and the protease inhibitor lopinavir/ritonavir should follow the same dosing titration/maintenance regimen used with AEDs that induce glucuronidation and increase clearance [see Dosage and Administration (2.1), Drug Interactions (7), Clinical Pharmacology (12.3)].

Table 6. Dosage Adjustments to LAMICTAL in Adults with Bipolar Disorder following Discontinuation of Psychotropic Medications
 | Discontinuation of Psychotropic Drugs (excluding Valproate,a Carbamazepine, Phenytoin, Phenobarbital, or Primidoneb) | After Discontinuation of Valproatea | After Discontinuation of Carbamazepine, Phenytoin, Phenobarbital, or Primidoneb
 | Discontinuation of Psychotropic Drugs (excluding Valproate,a Carbamazepine, Phenytoin, Phenobarbital, or Primidoneb) | Current Dose of LAMICTAL (mg/day); 100 | Current Dose of LAMICTAL (mg/day); 400
Week 1 | Maintain current dose of LAMICTAL | 150 | 400
Week 2 | Maintain current dose of LAMICTAL | 200 | 300
Week 3 onward | Maintain current dose of LAMICTAL | 200 | 200
a Valproate has been shown to inhibit glucuronidation and decrease the apparent clearance of lamotrigine [see Drug Interactions (7), Clinical Pharmacology (12.3)].
b Drugs that induce lamotrigine glucuronidation and increase clearance, other than the specified AEDs, include estrogen-containing products, including oral contraceptives, rifampin, and the protease inhibitors lopinavir/ritonavir and atazanavir/ritonavir. Dosing recommendations for oral contraceptives and the protease inhibitor atazanavir/ritonavir can be found in General Dosing Considerations [see Dosage and Administration (2.1)]. Patients on rifampin and the protease inhibitor lopinavir/ritonavir should follow the same dosing titration/maintenance regimen used with AEDs that induce glucuronidation and increase clearance [see Dosage and Administration (2.1), Drug Interactions (7), Clinical Pharmacology (12.3)].

2.5 Administration of LAMICTAL Tablets for Oral Suspension

LAMICTAL tablets for oral suspension may be swallowed whole, chewed, or dispersed in water or diluted fruit juice. If the tablets are chewed, consume a small amount of water or diluted fruit juice to aid in swallowing.

To disperse LAMICTAL tablets for oral suspension, add the tablets to a small amount of liquid (1 teaspoon, or enough to cover the medication). Approximately 1 minute later, when the tablets are completely dispersed, swirl the solution and consume the entire quantity immediately. No attempt should be made to administer partial quantities of the dispersed tablets.

2.6 Administration of LAMICTAL ODT Orally Disintegrating Tablets

LAMICTAL ODT orally disintegrating tablets should be placed onto the tongue and moved around in the mouth. The tablet will disintegrate rapidly, can be swallowed with or without water, and can be taken with or without food.

3 DOSAGE FORMS AND STRENGTHS

3.1 Tablets

25-mg, white, scored, shield-shaped tablets debossed with “LAMICTAL” and “25.”

100-mg, peach, scored, shield-shaped tablets debossed with “LAMICTAL” and “100.”

150-mg, cream, scored, shield-shaped tablets debossed with “LAMICTAL” and “150.”

200-mg, blue, scored, shield-shaped tablets debossed with “LAMICTAL” and “200.”

3.2 Tablets for Oral Suspension

2-mg, white to off-white, round tablets debossed with “LTG” over “2.”

5-mg, white to off-white, caplet-shaped tablets debossed with “GX CL2.”

25-mg, white, super elliptical-shaped tablets debossed with “GX CL5.”

3.3 Orally Disintegrating Tablets

25-mg, white to off-white, round, flat-faced, radius-edged tablets debossed with “LMT” on one side and “25” on the other side.

50-mg, white to off-white, round, flat-faced, radius-edged tablets debossed with “LMT” on one side and “50” on the other side.

100-mg, white to off-white, round, flat-faced, radius-edged tablets debossed with “LAMICTAL” on one side and “100” on the other side.

200-mg, white to off-white, round, flat-faced, radius-edged tablets debossed with “LAMICTAL” on one side and “200” on the other side.

4 CONTRAINDICATIONS

LAMICTAL is contraindicated in patients who have demonstrated hypersensitivity (e.g., rash, angioedema, acute urticaria, extensive pruritus, mucosal ulceration) to the drug or its ingredients [see Boxed Warning, Warnings and Precautions (5.1, 5.3)].

5 WARNINGS AND PRECAUTIONS

5.1 Serious Skin Rashes [see Boxed Warning]

Pediatric Population

The incidence of serious rash associated with hospitalization and discontinuation of LAMICTAL in a prospectively followed cohort of pediatric patients (aged 2 to 17 years) is approximately 0.3% to 0.8%. One rash-related death was reported in a prospectively followed cohort of 1,983 pediatric patients (aged 2 to 16 years) with epilepsy taking LAMICTAL as adjunctive therapy. Additionally, there have been rare cases of toxic epidermal necrolysis (TEN) with and without permanent sequelae and/or death in U.S. and foreign postmarketing experience.

There is evidence that the inclusion of valproate in a multidrug regimen increases the risk of serious, potentially life-threatening rash in pediatric patients. In pediatric patients who used valproate concomitantly for epilepsy, 1.2% (6 of 482) experienced a serious rash compared with 0.6% (6 of 952) patients not taking valproate.

Adult Population

Serious rash associated with hospitalization and discontinuation of LAMICTAL occurred in 0.3% (11 of 3,348) of adult patients who received LAMICTAL in premarketing clinical trials of epilepsy. In the bipolar and other mood disorders clinical trials, the rate of serious rash was 0.08% (1 of 1,233) of adult patients who received LAMICTAL as initial monotherapy and 0.13% (2 of 1,538) of adult patients who received LAMICTAL as adjunctive therapy. No fatalities occurred among these individuals. However, in worldwide postmarketing experience, rare cases of rash-related death have been reported, but their numbers are too few to permit a precise estimate of the rate.

Among the rashes leading to hospitalization were Stevens-Johnson syndrome, toxic epidermal necrolysis, angioedema, and those associated with multiorgan hypersensitivity [see Warnings and Precautions (5.3)].

Risk Factors

Concomitant Use of Valproate

There is evidence that the inclusion of valproate in a multidrug regimen increases the risk of serious, potentially life-threatening rash in adults. Specifically, of 584 patients administered LAMICTAL with valproate in epilepsy clinical trials, 6 (1%) were hospitalized in association with rash; in contrast, 4 (0.16%) of 2,398 clinical trial patients and volunteers administered LAMICTAL in the absence of valproate were hospitalized.

Patients with History of Allergy or Rash to Other Antiepileptic Drugs

The risk of rash may be increased in patients with a history of allergy or rash to other AEDs.

Not Adhering to the Recommended Dosage

The risk of rash is increased by both exceeding the recommended initial dose of LAMICTAL and exceeding the recommended dose escalation for LAMICTAL.

Patients with Genetic Variant Human Leukocyte Antigen (HLA)‑B*1502 Allele

Retrospective case-control studies in patients of certain Asian ancestry (e.g., Han Chinese and Thai) suggest that the HLA-B*1502 allele is associated with an increased risk (approximately 2‑3 times higher) of developing Stevens-Johnson syndrome (SJS)/toxic epidermal necrolysis (TEN) in patients using lamotrigine. The risks and benefits of therapy should be weighed when considering use of LAMICTAL in patients known to be positive for HLA-B*1502. Application of HLA genotyping as a screening tool has important limitations and must never substitute for appropriate clinical vigilance and patient management. Many HLA‑B*1502‑positive patients treated with LAMICTAL will not develop SJS/TEN or other hypersensitivity reactions, and these reactions can still occur in HLA‑B*1502‑negative patients of any ethnicity.

5.2 Hemophagocytic Lymphohistiocytosis

Hemophagocytic lymphohistiocytosis (HLH) has occurred in pediatric and adult patients taking LAMICTAL for various indications. HLH is a life-threatening syndrome of pathologic immune activation characterized by clinical signs and symptoms of extreme systemic inflammation. It is associated with high mortality rates if not recognized early and treated. Common findings include fever, hepatosplenomegaly, rash, lymphadenopathy, neurologic symptoms, cytopenias, high serum ferritin, hypertriglyceridemia, and liver function and coagulation abnormalities. In cases of HLH reported with LAMICTAL, patients have presented with signs of systemic inflammation (fever, rash, hepatosplenomegaly, and organ system dysfunction) and blood dyscrasias. Symptoms have been reported to occur within 8 to 24 days following the initiation of treatment. Patients who develop early manifestations of pathologic immune activation should be evaluated immediately, and a diagnosis of HLH should be considered. LAMICTAL should be discontinued if an alternative etiology for the signs or symptoms cannot be established.

5.3 Multiorgan Hypersensitivity Reactions and Organ Failure

Multiorgan hypersensitivity reactions, also known as drug reaction with eosinophilia and systemic symptoms (DRESS), have occurred with LAMICTAL. Some have been fatal or life threatening. DRESS typically, although not exclusively, presents with fever, rash, and/or lymphadenopathy in association with other organ system involvement, such as hepatitis, nephritis, hematologic abnormalities, myocarditis, or myositis, sometimes resembling an acute viral infection. Eosinophilia is often present. This disorder is variable in its expression, and other organ systems not noted here may be involved.

Fatalities associated with acute multiorgan failure and various degrees of hepatic failure have been reported in 2 of 3,796 adult patients and 4 of 2,435 pediatric patients who received LAMICTAL in epilepsy clinical trials. Rare fatalities from multiorgan failure have also been reported in postmarketing use.

Isolated liver failure without rash or involvement of other organs has also been reported with LAMICTAL.

It is important to note that early manifestations of hypersensitivity (e.g., fever, lymphadenopathy) may be present even though a rash is not evident. If such signs or symptoms are present, the patient should be evaluated immediately. LAMICTAL should be discontinued if an alternative etiology for the signs or symptoms cannot be established.

Prior to initiation of treatment with LAMICTAL, the patient should be instructed that a rash or other signs or symptoms of hypersensitivity (e.g., fever, lymphadenopathy) may herald a serious medical event and that the patient should report any such occurrence to a healthcare provider immediately.

5.4 Cardiac Rhythm and Conduction Abnormalities

In vitro testing showed that LAMICTAL exhibits Class IB antiarrhythmic activity at therapeutically relevant concentrations [see Clinical Pharmacology (12.2)]. Based on these in vitro findings, LAMICTAL could slow ventricular conduction (widen QRS) and induce proarrhythmia, which can lead to sudden death, in patients with clinically important structural or functional heart disease (i.e., patients with heart failure, valvular heart disease, congenital heart disease, conduction system disease, ventricular arrhythmias, cardiac channelopathies [e.g., Brugada syndrome], clinically important ischemic heart disease, or multiple risk factors for coronary artery disease). Any expected or observed benefit of LAMICTAL in an individual patient with clinically important structural or functional heart disease must be carefully weighed against the risks for serious arrythmias and/or death for that patient. Concomitant use of other sodium channel blockers may further increase the risk of proarrhythmia.

5.5 Blood Dyscrasias

There have been reports of blood dyscrasias that may or may not be associated with multiorgan hypersensitivity (also known as DRESS) [see Warnings and Precautions (5.3)]. These have included neutropenia, leukopenia, anemia, thrombocytopenia, pancytopenia, and, rarely, aplastic anemia and pure red cell aplasia.

5.6 Suicidal Behavior and Ideation

Antiepileptic drugs, including LAMICTAL, increase the risk of suicidal thoughts or behavior in patients taking these drugs for any indication. Patients treated with any AED for any indication should be monitored for the emergence or worsening of depression, suicidal thoughts or behavior, and/or any unusual changes in mood or behavior.

Pooled analyses of 199 placebo-controlled clinical trials (monotherapy and adjunctive therapy) of 11 different AEDs showed that patients randomized to 1 of the AEDs had approximately twice the risk (adjusted Relative Risk 1.8, 95% CI: 1.2, 2.7) of suicidal thinking or behavior compared with patients randomized to placebo. In these trials, which had a median treatment duration of 12 weeks, the estimated incidence of suicidal behavior or ideation among 27,863 AED-treated patients was 0.43%, compared with 0.24% among 16,029 placebo-treated patients, representing an increase of approximately 1 case of suicidal thinking or behavior for every 530 patients treated. There were 4 suicides in drug-treated patients in the trials and none in placebo-treated patients, but the number of events is too small to allow any conclusion about drug effect on suicide.

The increased risk of suicidal thoughts or behavior with AEDs was observed as early as 1 week after starting treatment with AEDs and persisted for the duration of treatment assessed. Because most trials included in the analysis did not extend beyond 24 weeks, the risk of suicidal thoughts or behavior beyond 24 weeks could not be assessed.

The risk of suicidal thoughts or behavior was generally consistent among drugs in the data analyzed. The finding of increased risk with AEDs of varying mechanism of action and across a range of indications suggests that the risk applies to all AEDs used for any indication. The risk did not vary substantially by age (5 to 100 years) in the clinical trials analyzed.

Table 7 shows absolute and relative risk by indication for all evaluated AEDs.

Table 7. Risk by Indication for Antiepileptic Drugs in the Pooled Analysis
Indication | Placebo Patients with Events per 1,000 Patients | Drug Patients with Events per 1,000 Patients | Relative Risk: Incidence of Events in Drug Patients/ Incidence in Placebo Patients | Risk Difference: Additional Drug Patients with Events per 1,000 Patients
Epilepsy | 1.0 | 3.4 | 3.5 | 2.4
Psychiatric | 5.7 | 8.5 | 1.5 | 2.9
Other | 1.0 | 1.8 | 1.9 | 0.9
Total | 2.4 | 4.3 | 1.8 | 1.9

The relative risk for suicidal thoughts or behavior was higher in clinical trials for epilepsy than in clinical trials for psychiatric or other conditions, but the absolute risk differences were similar for the epilepsy and psychiatric indications.

Anyone considering prescribing LAMICTAL or any other AED must balance the risk of suicidal thoughts or behavior with the risk of untreated illness. Epilepsy and many other illnesses for which AEDs are prescribed are themselves associated with morbidity and mortality and an increased risk of suicidal thoughts and behavior. Should suicidal thoughts and behavior emerge during treatment, the prescriber needs to consider whether the emergence of these symptoms in any given patient may be related to the illness being treated.

Patients, their caregivers, and families should be informed that AEDs increase the risk of suicidal thoughts and behavior and should be advised of the need to be alert for the emergence or worsening of the signs and symptoms of depression, any unusual changes in mood or behavior, the emergence of suicidal thoughts or suicidal behavior, or thoughts about self-harm. Behaviors of concern should be reported immediately to healthcare providers.

5.7 Aseptic Meningitis

Therapy with LAMICTAL increases the risk of developing aseptic meningitis. Because of the potential for serious outcomes of untreated meningitis due to other causes, patients should also be evaluated for other causes of meningitis and treated as appropriate.

Postmarketing cases of aseptic meningitis have been reported in pediatric and adult patients taking LAMICTAL for various indications. Symptoms upon presentation have included headache, fever, nausea, vomiting, and nuchal rigidity. Rash, photophobia, myalgia, chills, altered consciousness, and somnolence were also noted in some cases. Symptoms have been reported to occur within 1 day to one and a half months following the initiation of treatment. In most cases, symptoms were reported to resolve after discontinuation of LAMICTAL. Re-exposure resulted in a rapid return of symptoms (from within 30 minutes to 1 day following re-initiation of treatment) that were frequently more severe. Some of the patients treated with LAMICTAL who developed aseptic meningitis had underlying diagnoses of systemic lupus erythematosus or other autoimmune diseases.

Cerebrospinal fluid (CSF) analyzed at the time of clinical presentation in reported cases was characterized by a mild to moderate pleocytosis, normal glucose levels, and mild to moderate increase in protein. CSF white blood cell count differentials showed a predominance of neutrophils in a majority of the cases, although a predominance of lymphocytes was reported in approximately one third of the cases. Some patients also had new onset of signs and symptoms of involvement of other organs (predominantly hepatic and renal involvement), which may suggest that in these cases the aseptic meningitis observed was part of a hypersensitivity reaction [see Warnings and Precautions (5.3)].

5.8 Potential Medication Errors

Medication errors involving LAMICTAL have occurred. In particular, the names LAMICTAL or lamotrigine can be confused with the names of other commonly used medications. Medication errors may also occur between the different formulations of LAMICTAL. To reduce the potential of medication errors, write and say LAMICTAL clearly. Depictions of the LAMICTAL tablets, tablets for oral suspension, and orally disintegrating tablets can be found in the Medication Guide that accompanies the product to highlight the distinctive markings, colors, and shapes that serve to identify the different presentations of the drug and thus may help reduce the risk of medication errors. To avoid the medication error of using the wrong drug or formulation, patients should be strongly advised to visually inspect their tablets to verify that they are LAMICTAL, as well as the correct formulation of LAMICTAL, each time they fill their prescription.

5.9 Concomitant Use with Estrogen-Containing Products, Including Oral Contraceptives

Some estrogen-containing oral contraceptives have been shown to decrease serum concentrations of lamotrigine [see Clinical Pharmacology (12.3)]. Dosage adjustments will be necessary in most patients who start or stop estrogen-containing oral contraceptives while taking LAMICTAL [see Dosage and Administration (2.1)]. During the week of inactive hormone preparation (pill-free week) of oral contraceptive therapy, plasma lamotrigine levels are expected to rise, as much as doubling at the end of the week. Adverse reactions consistent with elevated levels of lamotrigine, such as dizziness, ataxia, and diplopia, could occur. Other oral contraceptive and other estrogen-containing therapies (such as HRT) have not been studied, though they may similarly affect lamotrigine pharmacokinetic parameters.

5.10 Withdrawal Seizures

As with other AEDs, LAMICTAL should not be abruptly discontinued. In patients with epilepsy there is a possibility of increasing seizure frequency. In clinical trials in adults with bipolar disorder, 2 patients experienced seizures shortly after abrupt withdrawal of LAMICTAL. Unless safety concerns require a more rapid withdrawal, the dose of LAMICTAL should be tapered over a period of at least 2 weeks (approximately 50% reduction per week) [see Dosage and Administration (2.1)].

5.11 Status Epilepticus

Valid estimates of the incidence of treatment-emergent status epilepticus among patients treated with LAMICTAL are difficult to obtain because reporters participating in clinical trials did not all employ identical rules for identifying cases. At a minimum, 7 of 2,343 adult patients had episodes that could unequivocally be described as status epilepticus. In addition, a number of reports of variably defined episodes of seizure exacerbation (e.g., seizure clusters, seizure flurries) were made.

5.12 Addition of LAMICTAL to a Multidrug Regimen that Includes Valproate

Because valproate reduces the clearance of lamotrigine, the dosage of LAMICTAL in the presence of valproate is less than half of that required in its absence [see Dosage and Administration (2.2, 2.3, 2.4), Drug Interactions (7)].

5.13 Binding in the Eye and Other Melanin-Containing Tissues

Because lamotrigine binds to melanin, it could accumulate in melanin-rich tissues over time. This raises the possibility that lamotrigine may cause toxicity in these tissues after extended use. Although ophthalmological testing was performed in 1 controlled clinical trial, the testing was inadequate to exclude subtle effects or injury occurring after long-term exposure. Moreover, the capacity of available tests to detect potentially adverse consequences, if any, of lamotrigine’s binding to melanin is unknown [see Clinical Pharmacology (12.2)].

Accordingly, although there are no specific recommendations for periodic ophthalmological monitoring, prescribers should be aware of the possibility of long-term ophthalmologic effects.

5.14 Laboratory Tests

False-Positive Drug Test Results

Lamotrigine has been reported to interfere with the assay used in some rapid urine drug screens, which can result in false-positive readings, particularly for phencyclidine (PCP). A more specific analytical method should be used to confirm a positive result.

Plasma Concentrations of Lamotrigine

The value of monitoring plasma concentrations of lamotrigine in patients treated with LAMICTAL has not been established. Because of the possible pharmacokinetic interactions between lamotrigine and other drugs, including AEDs (see Table 13), monitoring of the plasma levels of lamotrigine and concomitant drugs may be indicated, particularly during dosage adjustments. In general, clinical judgment should be exercised regarding monitoring of plasma levels of lamotrigine and other drugs and whether or not dosage adjustments are necessary.

6 ADVERSE REACTIONS

The following serious adverse reactions are described in more detail in the Warnings and Precautions section of the labeling:

- Serious Skin Rashes [see Warnings and Precautions (5.1)]
- Hemophagocytic Lymphohistiocytosis [see Warnings and Precautions (5.2)]
- Multiorgan Hypersensitivity Reactions and Organ Failure [see Warnings and Precautions (5.3)]
- Cardiac Rhythm and Conduction Abnormalities [see Warnings and Precautions (5.4)]
- Blood Dyscrasias [see Warnings and Precautions (5.5)]
- Suicidal Behavior and Ideation [see Warnings and Precautions (5.6)]
- Aseptic Meningitis [see Warnings and Precautions (5.7)]
- Withdrawal Seizures [see Warnings and Precautions (5.10)]
- Status Epilepticus [see Warnings and Precautions (5.11)]

6.1 Clinical Trial Experience

Because clinical trials are conducted under widely varying conditions, adverse reaction rates observed in the clinical trials of a drug cannot be directly compared with rates in the clinical trials of another drug and may not reflect the rates observed in practice.

Epilepsy

Most Common Adverse Reactions in All Clinical Trials: Adjunctive Therapy in Adults with Epilepsy: The most commonly observed (≥5% for LAMICTAL and more common on drug than placebo) adverse reactions seen in association with LAMICTAL during adjunctive therapy in adults and not seen at an equivalent frequency among placebo-treated patients were: dizziness, ataxia, somnolence, headache, diplopia, blurred vision, nausea, vomiting, and rash. Dizziness, diplopia, ataxia, blurred vision, nausea, and vomiting were dose related. Dizziness, diplopia, ataxia, and blurred vision occurred more commonly in patients receiving carbamazepine with LAMICTAL than in patients receiving other AEDs with LAMICTAL. Clinical data suggest a higher incidence of rash, including serious rash, in patients receiving concomitant valproate than in patients not receiving valproate [see Warnings and Precautions (5.1)].

Approximately 11% of the 3,378 adult patients who received LAMICTAL as adjunctive therapy in premarketing clinical trials discontinued treatment because of an adverse reaction. The adverse reactions most commonly associated with discontinuation were rash (3.0%), dizziness (2.8%), and headache (2.5%).

In a dose-response trial in adults, the rate of discontinuation of LAMICTAL for dizziness, ataxia, diplopia, blurred vision, nausea, and vomiting was dose related.

Monotherapy in Adults with Epilepsy: The most commonly observed (≥5% for LAMICTAL and more common on drug than placebo) adverse reactions seen in association with the use of LAMICTAL during the monotherapy phase of the controlled trial in adults not seen at an equivalent rate in the control group were vomiting, coordination abnormality, dyspepsia, nausea, dizziness, rhinitis, anxiety, insomnia, infection, pain, weight decrease, chest pain, and dysmenorrhea. The most commonly observed (≥5% for LAMICTAL and more common on drug than placebo) adverse reactions associated with the use of LAMICTAL during the conversion to monotherapy (add-on) period, not seen at an equivalent frequency among low-dose valproate-treated patients, were dizziness, headache, nausea, asthenia, coordination abnormality, vomiting, rash, somnolence, diplopia, ataxia, accidental injury, tremor, blurred vision, insomnia, nystagmus, diarrhea, lymphadenopathy, pruritus, and sinusitis.

Approximately 10% of the 420 adult patients who received LAMICTAL as monotherapy in premarketing clinical trials discontinued treatment because of an adverse reaction. The adverse reactions most commonly associated with discontinuation were rash (4.5%), headache (3.1%), and asthenia (2.4%).

Adjunctive Therapy in Pediatric Patients with Epilepsy: The most commonly observed (≥5% for LAMICTAL and more common on drug than placebo) adverse reactions seen in association with the use of LAMICTAL as adjunctive treatment in pediatric patients aged 2 to 16 years and not seen at an equivalent rate in the control group were infection, vomiting, rash, fever, somnolence, accidental injury, dizziness, diarrhea, abdominal pain, nausea, ataxia, tremor, asthenia, bronchitis, flu syndrome, and diplopia.

In 339 patients aged 2 to 16 years with partial-onset seizures or generalized seizures of Lennox-Gastaut syndrome, 4.2% of patients on LAMICTAL and 2.9% of patients on placebo discontinued due to adverse reactions. The most commonly reported adverse reaction that led to discontinuation of LAMICTAL was rash.

Approximately 11.5% of the 1,081 pediatric patients aged 2 to 16 years who received LAMICTAL as adjunctive therapy in premarketing clinical trials discontinued treatment because of an adverse reaction. The adverse reactions most commonly associated with discontinuation were rash (4.4%), reaction aggravated (1.7%), and ataxia (0.6%).

Controlled Adjunctive Clinical Trials in Adults with Epilepsy: Table 8 lists adverse reactions that occurred in adult patients with epilepsy treated with LAMICTAL in placebo-controlled trials. In these trials, either LAMICTAL or placebo was added to the patient’s current AED therapy.

Table 8. Adverse Reactions in Pooled, Placebo-Controlled Adjunctive Trials in Adult Patients with Epilepsya,b
Body System/ Adverse Reaction | Percent of Patients Receiving Adjunctive LAMICTAL; (n = 711) | Percent of Patients Receiving Adjunctive Placebo; (n = 419)
Body as a whole
Headache | 29 | 19
Flu syndrome | 7 | 6
Fever | 6 | 4
Abdominal pain | 5 | 4
Neck pain | 2 | 1
Reaction aggravated (seizure exacerbation) | 2 | 1
Digestive
Nausea | 19 | 10
Vomiting | 9 | 4
Diarrhea | 6 | 4
Dyspepsia | 5 | 2
Constipation | 4 | 3
Anorexia | 2 | 1
Musculoskeletal
Arthralgia | 2 | 0
Nervous
Dizziness | 38 | 13
Ataxia | 22 | 6
Somnolence | 14 | 7
Incoordination | 6 | 2
Insomnia | 6 | 2
Tremor | 4 | 1
Depression | 4 | 3
Anxiety | 4 | 3
Convulsion | 3 | 1
Irritability | 3 | 2
Speech disorder | 3 | 0
Concentration disturbance | 2 | 1
Respiratory
Rhinitis | 14 | 9
Pharyngitis | 10 | 9
Cough increased | 8 | 6
Skin and appendages
Rash | 10 | 5
Pruritus | 3 | 2
Special senses
Diplopia | 28 | 7
Blurred vision | 16 | 5
Vision abnormality | 3 | 1
Urogenital
Female patients only | (n = 365) | (n = 207)
Dysmenorrhea | 7 | 6
Vaginitis | 4 | 1
Amenorrhea | 2 | 1
a Adverse reactions that occurred in at least 2% of patients treated with LAMICTAL and at a greater incidence than placebo.
b Patients in these adjunctive trials were receiving 1 to 3 of the concomitant AEDs carbamazepine, phenytoin, phenobarbital, or primidone in addition to LAMICTAL or placebo. Patients may have reported multiple adverse reactions during the trial or at discontinuation; thus, patients may be included in more than 1 category.

In a randomized, parallel trial comparing placebo with 300 and 500 mg/day of LAMICTAL, some of the more common drug-related adverse reactions were dose related (see Table 9).

Table 9. Dose-Related Adverse Reactions from a Randomized, Placebo-Controlled, Adjunctive Trial in Adults with Epilepsy
Adverse Reaction | Percent of Patients Experiencing Adverse Reactions
Adverse Reaction | Placebo; (n = 73) | LAMICTAL 300 mg; (n = 71) | LAMICTAL 500 mg; (n = 72)
Ataxia | 10 | 10 | 28a,b
Blurred vision | 10 | 11 | 25a,b
Diplopia | 8 | 24a | 49a,b
Dizziness | 27 | 31 | 54a,b
Nausea | 11 | 18 | 25a
Vomiting | 4 | 11 | 18a
a Significantly greater than placebo group (P<0.05).
b Significantly greater than group receiving LAMICTAL 300 mg (P<0.05).

The overall adverse reaction profile for LAMICTAL was similar between females and males and was independent of age. Because the largest non-Caucasian racial subgroup was only 6% of patients exposed to LAMICTAL in placebo-controlled trials, there are insufficient data to support a statement regarding the distribution of adverse reaction reports by race. Generally, females receiving either LAMICTAL as adjunctive therapy or placebo were more likely to report adverse reactions than males. The only adverse reaction for which the reports on LAMICTAL were >10% more frequent in females than males (without a corresponding difference by gender on placebo) was dizziness (difference = 16.5%). There was little difference between females and males in the rates of discontinuation of LAMICTAL for individual adverse reactions.

Controlled Monotherapy Trial in Adults with Partial-Onset Seizures: Table 10 lists adverse reactions that occurred in patients with epilepsy treated with monotherapy with LAMICTAL in a double-blind trial following discontinuation of either concomitant carbamazepine or phenytoin not seen at an equivalent frequency in the control group.

Table 10. Adverse Reactions in a Controlled Monotherapy Trial in Adult Patients with Partial-Onset Seizuresa,b
Body System/ Adverse Reaction | Percent of Patients Receiving LAMICTALc as Monotherapy; (n = 43) | Percent of Patients Receiving Low-Dose Valproated Monotherapy; (n = 44)
Body as a whole
Pain | 5 | 0
Infection | 5 | 2
Chest pain | 5 | 2
Digestive
Vomiting | 9 | 0
Dyspepsia | 7 | 2
Nausea | 7 | 2
Metabolic and nutritional
Weight decrease | 5 | 2
Nervous
Coordination abnormality | 7 | 0
Dizziness | 7 | 0
Anxiety | 5 | 0
Insomnia | 5 | 2
Respiratory
Rhinitis | 7 | 2
Urogenital (female patients only) | (n = 21) | (n = 28)
Dysmenorrhea | 5 | 0
a Adverse reactions that occurred in at least 5% of patients treated with LAMICTAL and at a greater incidence than valproate-treated patients.
b Patients in this trial were converted to LAMICTAL or valproate monotherapy from adjunctive therapy with carbamazepine or phenytoin. Patients may have reported multiple adverse reactions during the trial; thus, patients may be included in more than 1 category.
c Up to 500 mg/day.
d 1,000 mg/day.

Adverse reactions that occurred with a frequency of <5% and >2% of patients receiving LAMICTAL and numerically more frequent than placebo were:

Body as a Whole: Asthenia, fever.

Digestive: Anorexia, dry mouth, rectal hemorrhage, peptic ulcer.

Metabolic and Nutritional: Peripheral edema.

Nervous System: Amnesia, ataxia, depression, hypesthesia, libido increase, decreased reflexes, increased reflexes, nystagmus, irritability, suicidal ideation.

Respiratory: Epistaxis, bronchitis, dyspnea.

Skin and Appendages: Contact dermatitis, dry skin, sweating.

Special Senses: Vision abnormality.

Incidence in Controlled Adjunctive Trials in Pediatric Patients with Epilepsy: Table 11 lists adverse reactions that occurred in 339 pediatric patients with partial-onset seizures or generalized seizures of Lennox-Gastaut syndrome who received LAMICTAL up to 15 mg/kg/day or a maximum of 750 mg/day.

Table 11. Adverse Reactions in Pooled, Placebo-Controlled, Adjunctive Trials in Pediatric Patients with Epilepsya
Body System/ Adverse Reaction | Percent of Patients Receiving LAMICTAL; (n = 168) | Percent of Patients Receiving Placebo; (n = 171)
Body as a whole
Infection | 20 | 17
Fever | 15 | 14
Accidental injury | 14 | 12
Abdominal pain | 10 | 5
Asthenia | 8 | 4
Flu syndrome | 7 | 6
Pain | 5 | 4
Facial edema | 2 | 1
Photosensitivity | 2 | 0
Cardiovascular
Hemorrhage | 2 | 1
Digestive
Vomiting | 20 | 16
Diarrhea | 11 | 9
Nausea | 10 | 2
Constipation | 4 | 2
Dyspepsia | 2 | 1
Hemic and lymphatic
Lymphadenopathy | 2 | 1
Metabolic and nutritional
Edema | 2 | 0
Nervous system
Somnolence | 17 | 15
Dizziness | 14 | 4
Ataxia | 11 | 3
Tremor | 10 | 1
Emotional lability | 4 | 2
Gait abnormality | 4 | 2
Thinking abnormality | 3 | 2
Convulsions | 2 | 1
Nervousness | 2 | 1
Vertigo | 2 | 1
Respiratory
Pharyngitis | 14 | 11
Bronchitis | 7 | 5
Increased cough | 7 | 6
Sinusitis | 2 | 1
Bronchospasm | 2 | 1
Skin
Rash | 14 | 12
Eczema | 2 | 1
Pruritus | 2 | 1
Special senses
Diplopia | 5 | 1
Blurred vision | 4 | 1
Visual abnormality | 2 | 0
Urogenital
Male and female patients
Urinary tract infection | 3 | 0
a Adverse reactions that occurred in at least 2% of patients treated with LAMICTAL and at a greater incidence than placebo.

Bipolar Disorder in Adults

The most common adverse reactions seen in association with the use of LAMICTAL as monotherapy (100 to 400 mg/day) in adult patients (aged 18 to 82 years) with bipolar disorder in the 2 double-blind, placebo-controlled trials of 18 months’ duration are included in Table 12. Adverse reactions that occurred in at least 5% of patients and were numerically more frequent during the dose-escalation phase of LAMICTAL in these trials (when patients may have been receiving concomitant medications) compared with the monotherapy phase were: headache (25%), rash (11%), dizziness (10%), diarrhea (8%), dream abnormality (6%), and pruritus (6%).

During the monotherapy phase of the double-blind, placebo-controlled trials of 18 months’ duration, 13% of 227 patients who received LAMICTAL (100 to 400 mg/day), 16% of 190 patients who received placebo, and 23% of 166 patients who received lithium discontinued therapy because of an adverse reaction. The adverse reactions that most commonly led to discontinuation of LAMICTAL were rash (3%) and mania/hypomania/mixed mood adverse reactions (2%). Approximately 16% of 2,401 patients who received LAMICTAL (50 to 500 mg/day) for bipolar disorder in premarketing trials discontinued therapy because of an adverse reaction, most commonly due to rash (5%) and mania/hypomania/mixed mood adverse reactions (2%).

The overall adverse reaction profile for LAMICTAL was similar between females and males, between elderly and nonelderly patients, and among racial groups.

Table 12. Adverse Reactions in 2 Placebo-Controlled Trials in Adult Patients with Bipolar I Disordera,b
Body System/ Adverse Reaction | Percent of Patients Receiving LAMICTAL; (n = 227) | Percent of Patients Receiving Placebo; (n = 190)
General
Back pain | 8 | 6
Fatigue | 8 | 5
Abdominal pain | 6 | 3
Digestive
Nausea | 14 | 11
Constipation | 5 | 2
Vomiting | 5 | 2
Nervous System
Insomnia | 10 | 6
Somnolence | 9 | 7
Xerostomia (dry mouth) | 6 | 4
Respiratory
Rhinitis | 7 | 4
Exacerbation of cough | 5 | 3
Pharyngitis | 5 | 4
Skin
Rash (nonserious)c | 7 | 5
a Adverse reactions that occurred in at least 5% of patients treated with LAMICTAL and at a greater incidence than placebo.
b Patients in these trials were converted to LAMICTAL (100 to 400 mg/day) or placebo monotherapy from add-on therapy with other psychotropic medications. Patients may have reported multiple adverse reactions during the trial; thus, patients may be included in more than 1 category.
c In the overall bipolar and other mood disorders clinical trials, the rate of serious rash was 0.08% (1 of 1,233) of adult patients who received LAMICTAL as initial monotherapy and 0.13% (2 of 1,538) of adult patients who received LAMICTAL as adjunctive therapy [see Warnings and Precautions (5.1)].

Other reactions that occurred in 5% or more patients but equally or more frequently in the placebo group included: dizziness, mania, headache, infection, influenza, pain, accidental injury, diarrhea, and dyspepsia.

Adverse reactions that occurred with a frequency of <5% and >1% of patients receiving LAMICTAL and numerically more frequent than placebo were:

General: Fever, neck pain.

Cardiovascular: Migraine.

Digestive: Flatulence.

Metabolic and Nutritional: Weight gain, edema.

Musculoskeletal: Arthralgia, myalgia.

Nervous System: Amnesia, depression, agitation, emotional lability, dyspraxia, abnormal thoughts, dream abnormality, hypoesthesia.

Respiratory: Sinusitis.

Urogenital: Urinary frequency.

Adverse Reactions following Abrupt Discontinuation: In the 2 controlled clinical trials, there was no increase in the incidence, severity, or type of adverse reactions in patients with bipolar disorder after abruptly terminating therapy with LAMICTAL. In the clinical development program in adults with bipolar disorder, 2 patients experienced seizures shortly after abrupt withdrawal of LAMICTAL [see Warnings and Precautions (5.10)].

Mania/Hypomania/Mixed Episodes: During the double-blind, placebo-controlled clinical trials in bipolar I disorder in which adults were converted to monotherapy with LAMICTAL (100 to 400 mg/day) from other psychotropic medications and followed for up to 18 months, the rates of manic or hypomanic or mixed mood episodes reported as adverse reactions were 5% for patients treated with LAMICTAL (n = 227), 4% for patients treated with lithium (n = 166), and 7% for patients treated with placebo (n = 190). In all bipolar controlled trials combined, adverse reactions of mania (including hypomania and mixed mood episodes) were reported in 5% of patients treated with LAMICTAL (n = 956), 3% of patients treated with lithium (n = 280), and 4% of patients treated with placebo (n = 803).

6.2 Other Adverse Reactions Observed in All Clinical Trials

LAMICTAL has been administered to 6,694 individuals for whom complete adverse reaction data was captured during all clinical trials, only some of which were placebo controlled. During these trials, all adverse reactions were recorded by the clinical investigators using terminology of their own choosing. To provide a meaningful estimate of the proportion of individuals having adverse reactions, similar types of adverse reactions were grouped into a smaller number of standardized categories using modified COSTART dictionary terminology. The frequencies presented represent the proportion of the 6,694 individuals exposed to LAMICTAL who experienced an event of the type cited on at least 1 occasion while receiving LAMICTAL. All reported adverse reactions are included except those already listed in the previous tables or elsewhere in the labeling, those too general to be informative, and those not reasonably associated with the use of the drug.

Adverse reactions are further classified within body system categories and enumerated in order of decreasing frequency using the following definitions: frequent adverse reactions are defined as those occurring in at least 1/100 patients; infrequent adverse reactions are those occurring in 1/100 to 1/1,000 patients; rare adverse reactions are those occurring in fewer than 1/1,000 patients.

Body as a Whole

Infrequent: Allergic reaction, chills, malaise.

Cardiovascular System

Infrequent: Flushing, hot flashes, hypertension, palpitations, postural hypotension, syncope, tachycardia, vasodilation.

Dermatological

Infrequent: Acne, alopecia, hirsutism, maculopapular rash, skin discoloration, urticaria.

Rare: Angioedema, erythema, exfoliative dermatitis, fungal dermatitis, herpes zoster, leukoderma, multiforme erythema, petechial rash, pustular rash, Stevens-Johnson syndrome, vesiculobullous rash.

Digestive System

Infrequent: Dysphagia, eructation, gastritis, gingivitis, increased appetite, increased salivation, liver function tests abnormal, mouth ulceration.

Rare: Gastrointestinal hemorrhage, glossitis, gum hemorrhage, gum hyperplasia, hematemesis, hemorrhagic colitis, hepatitis, melena, stomach ulcer, stomatitis, tongue edema.

Endocrine System

Rare: Goiter, hypothyroidism.

Hematologic and Lymphatic System

Infrequent: Ecchymosis, leukopenia.

Rare: Anemia, eosinophilia, fibrin decrease, fibrinogen decrease, iron deficiency anemia, leukocytosis, lymphocytosis, macrocytic anemia, petechia, thrombocytopenia.

Metabolic and Nutritional Disorders

Infrequent: Aspartate transaminase increased.

Rare: Alcohol intolerance, alkaline phosphatase increase, alanine transaminase increase, bilirubinemia, general edema, gamma glutamyl transpeptidase increase, hyperglycemia.

Musculoskeletal System

Infrequent: Arthritis, leg cramps, myasthenia, twitching.

Rare: Bursitis, muscle atrophy, pathological fracture, tendinous contracture.

Nervous System

Frequent: Confusion, paresthesia.

Infrequent: Akathisia, apathy, aphasia, central nervous system depression, depersonalization, dysarthria, dyskinesia, euphoria, hallucinations, hostility, hyperkinesia, hypertonia, libido decreased, memory decrease, mind racing, movement disorder, myoclonus, panic attack, paranoid reaction, personality disorder, psychosis, sleep disorder, stupor, suicidal ideation.

Rare: Choreoathetosis, delirium, delusions, dysphoria, dystonia, extrapyramidal syndrome, faintness, grand mal convulsions, hemiplegia, hyperalgesia, hyperesthesia, hypokinesia, hypotonia, manic depression reaction, muscle spasm, neuralgia, neurosis, paralysis, peripheral neuritis.

Respiratory System

Infrequent: Yawn.

Rare: Hiccup, hyperventilation.

Special Senses

Frequent: Amblyopia.

Infrequent: Abnormality of accommodation, conjunctivitis, dry eyes, ear pain, photophobia, taste perversion, tinnitus.

Rare: Deafness, lacrimation disorder, oscillopsia, parosmia, ptosis, strabismus, taste loss, uveitis, visual field defect.

Urogenital System

Infrequent: Abnormal ejaculation, hematuria, impotence, menorrhagia, polyuria, urinary incontinence.

Rare: Acute kidney failure, anorgasmia, breast abscess, breast neoplasm, creatinine increase, cystitis, dysuria, epididymitis, female lactation, kidney failure, kidney pain, nocturia, urinary retention, urinary urgency.

6.3 Postmarketing Experience

The following adverse reactions have been identified during postapproval use of LAMICTAL. Because these reactions are reported voluntarily from a population of uncertain size, it is not always possible to reliably estimate their frequency or establish a causal relationship to drug exposure.

Blood and Lymphatic

Agranulocytosis, hemolytic anemia, lymphadenopathy not associated with hypersensitivity disorder, pseudolymphoma.

Gastrointestinal

Esophagitis.

Hepatobiliary Tract and Pancreas

Pancreatitis.

Immunologic

Hypogammaglobulinemia, lupus-like reaction, vasculitis.

Lower Respiratory

Apnea.

Musculoskeletal

Rhabdomyolysis has been observed in patients experiencing hypersensitivity reactions.

Nervous System

Aggression, exacerbation of Parkinsonian symptoms in patients with pre-existing Parkinson’s disease, tics.

Non-site Specific

Progressive immunosuppression.

Renal and Urinary Disorders

Tubulointerstitial nephritis (has been reported alone and in association with uveitis).

Skin and subcutaneous tissue disorders

Photosensitivity reaction

7 DRUG INTERACTIONS

Significant drug interactions with LAMICTAL are summarized in this section.

Uridine 5´-diphospho-glucuronyl transferases (UGT) have been identified as the enzymes responsible for metabolism of lamotrigine. Drugs that induce or inhibit glucuronidation may, therefore, affect the apparent clearance of lamotrigine. Strong or moderate inducers of the cytochrome P450 3A4 (CYP3A4) enzyme, which are also known to induce UGT, may also enhance the metabolism of lamotrigine.

Those drugs that have been demonstrated to have a clinically significant impact on lamotrigine metabolism are outlined in Table 13. Specific dosing guidance for these drugs is provided in the Dosage and Administration section, and, for women taking estrogen‑containing products, including oral contraceptives, in the Warnings and Precautions section [see Dosage and Administration (2.1), Warnings and Precautions (5.9)].

Additional details of these drug interaction studies are provided in the Clinical Pharmacology section [see Clinical Pharmacology (12.3)].

Table 13. Established and Other Potentially Significant Drug Interactions
Concomitant Drug | Effect on Concentration of Lamotrigine or Concomitant Drug | Clinical Comment
Estrogen-containing oral contraceptive preparations containing 30 mcg ethinylestradiol and 150 mcg levonorgestrel | ↓ lamotrigine; ↓ levonorgestrel | Decreased lamotrigine concentrations approximately 50%.; Decrease in levonorgestrel component by 19%.
Carbamazepine and carbamazepine epoxide | ↓ lamotrigine; ? carbamazepine epoxide | Addition of carbamazepine decreases lamotrigine concentration approximately 40%.; May increase carbamazepine epoxide levels.
Lopinavir/ritonavir | ↓ lamotrigine | Decreased lamotrigine concentration approximately 50%.
Atazanavir/ritonavir | ↓ lamotrigine | Decreased lamotrigine AUC approximately 32%.
Phenobarbital/primidone | ↓ lamotrigine | Decreased lamotrigine concentration approximately 40%.
Phenytoin | ↓ lamotrigine | Decreased lamotrigine concentration approximately 40%.
Rifampin | ↓ lamotrigine | Decreased lamotrigine AUC approximately 40%.
Valproate | ↑ lamotrigine; ? valproate | Increased lamotrigine concentrations slightly more than 2-fold.; There are conflicting study results regarding effect of lamotrigine on valproate concentrations: 1) a mean 25% decrease in valproate concentrations in healthy volunteers, 2) no change in valproate concentrations in controlled clinical trials in patients with epilepsy.
↓ = Decreased (induces lamotrigine glucuronidation).
↑ = Increased (inhibits lamotrigine glucuronidation).
? = Conflicting data.

Effect of LAMICTAL on Organic Cationic Transporter 2 Substrates

Lamotrigine is an inhibitor of renal tubular secretion via organic cationic transporter 2 (OCT2) proteins [see Clinical Pharmacology (12.3)]. This may result in increased plasma levels of certain drugs that are substantially excreted via this route. Coadministration of LAMICTAL with OCT2 substrates with a narrow therapeutic index (e.g., dofetilide) is not recommended.

8 USE IN SPECIFIC POPULATIONS

8.1 Pregnancy

Pregnancy Exposure Registry

There is a pregnancy exposure registry that monitors pregnancy outcomes in women exposed to AEDs, including LAMICTAL, during pregnancy. Encourage women who are taking LAMICTAL during pregnancy to enroll in the North American Antiepileptic Drug (NAAED) Pregnancy Registry by calling 1-888-233-2334 or visiting http://www.aedpregnancyregistry.org/.

Risk Summary

Data from several prospective pregnancy exposure registries and epidemiological studies of pregnant women have not detected an increased frequency of major congenital malformations or a consistent pattern of malformations among women exposed to lamotrigine compared with the general population (see Data). The majority of LAMICTAL pregnancy exposure data are from women with epilepsy. In animal studies, administration of lamotrigine during pregnancy resulted in developmental toxicity (increased mortality, decreased body weight, increased structural variation, neurobehavioral abnormalities) at doses lower than those administered clinically.

Lamotrigine decreased fetal folate concentrations in rats, an effect known to be associated with adverse pregnancy outcomes in animals and humans (see Data).

In the U.S. general population, the estimated background risk of major birth defects and miscarriage in clinically recognized pregnancies is 2% to 4% and 15% to 20%, respectively.

Clinical Considerations

Disease-associated Maternal and/or Embryofetal Risk

Epilepsy, with or without exposure to antiepileptic drugs, has been associated with several adverse outcomes during pregnancy, including preeclampsia, preterm labor, antepartum and postpartum hemorrhage, placental abruption, poor fetal growth, prematurity, fetal death, and maternal mortality. The risk of maternal or fetal injury may be greatest for patients with untreated or poorly controlled convulsive seizures. Women with epilepsy who become pregnant should not abruptly discontinue antiepileptic drugs, including LAMICTAL, due to the risk of status epilepticus or severe seizures, which may be life-threatening [see Warnings and Precautions (5.10)].

Dose Adjustments During Pregnancy and the Postpartum Period

As with other AEDs, physiological changes during pregnancy may affect lamotrigine concentrations and/or therapeutic effect. There have been reports of decreased lamotrigine concentrations during pregnancy and restoration of pre-pregnancy concentrations after delivery. Dose adjustments may be necessary to maintain clinical response.

Data

Human Data: Data from several international pregnancy registries have not shown an increased risk for malformations overall. The International Lamotrigine Pregnancy Registry reported major congenital malformations in 2.2% (95% CI: 1.6%, 3.1%) of 1,558 infants exposed to lamotrigine monotherapy in the first trimester of pregnancy. The NAAED Pregnancy Registry reported major congenital malformations among 2.0% of 1,562 infants exposed to lamotrigine monotherapy in the first trimester. EURAP, a large international pregnancy registry focused outside of North America, reported major birth defects in 2.9% (95% CI: 2.3%, 3.7%) of 2,514 exposures to lamotrigine monotherapy in the first trimester. The frequency of major congenital malformations was similar to estimates from the general population.

The NAAED Pregnancy Registry observed an increased risk of isolated oral clefts: among 2,200 infants exposed to lamotrigine early in pregnancy, the risk of oral clefts was 3.2 per 1,000 (95% CI: 1.4, 6.3), a 3-fold increased risk versus unexposed healthy controls. This finding has not been observed in other large international pregnancy registries. Furthermore, a case-control study based on 21 congenital anomaly registries covering over 10 million births in Europe reported an adjusted odds ratio for isolated oral clefts with lamotrigine exposure of 1.45 (95% CI: 0.8, 2.63).

Several meta-analyses have not reported an increased risk of major congenital malformations following lamotrigine exposure in pregnancy compared with healthy and disease-matched controls. No patterns of specific malformation types were observed.

The same meta-analyses evaluated the risk of additional maternal and infant outcomes including fetal death, stillbirth, preterm birth, small for gestational age, and neurodevelopmental delay. Although there are no data suggesting an increased risk of these outcomes with lamotrigine monotherapy exposure, differences in outcome definition, ascertainment methods, and comparator groups limit the conclusions that can be drawn.

Animal Data: When lamotrigine was administered to pregnant mice, rats, or rabbits during the period of organogenesis (oral doses of up to 125, 25, and 30 mg/kg, respectively), reduced fetal body weight and increased incidences of fetal skeletal variations were seen in mice and rats at doses that were also maternally toxic. The no-effect doses for embryofetal developmental toxicity in mice, rats, and rabbits (75, 6.25, and 30 mg/kg, respectively) are similar to (mice and rabbits) or less than (rats) the human dose of 400 mg/day on a body surface area (mg/m^2) basis.

In a study in which pregnant rats were administered lamotrigine (oral doses of 0, 5, or 25 mg/kg) during the period of organogenesis and offspring were evaluated postnatally, neurobehavioral abnormalities were observed in exposed offspring at both doses. The lowest effect dose for developmental neurotoxicity in rats is less than the human dose of 400 mg/day on a mg/m^2 basis. Maternal toxicity was observed at the higher dose tested.

When pregnant rats were administered lamotrigine (oral doses of 0, 5, 10, or 20 mg/kg) during the latter part of gestation and throughout lactation, increased offspring mortality (including stillbirths) was seen at all doses. The lowest effect dose for pre- and post-natal developmental toxicity in rats is less than the human dose of 400 mg/day on a mg/m^2 basis. Maternal toxicity was observed at the 2 highest doses tested.

When administered to pregnant rats, lamotrigine decreased fetal folate concentrations at doses greater than or equal to 5 mg/kg/day, which is less than the human dose of 400 mg/day on a mg/m^2 basis.

8.2 Lactation

Risk Summary

Lamotrigine is present in milk from lactating women taking LAMICTAL (see Data). Neonates and young infants are at risk for high serum levels because maternal serum and milk levels can rise to high levels postpartum if lamotrigine dosage has been increased during pregnancy but is not reduced after delivery to the pre-pregnancy dosage. Glucuronidation is required for drug clearance. Glucuronidation capacity is immature in the infant and this may also contribute to the level of lamotrigine exposure. Events including rash, apnea, drowsiness, poor sucking, and poor weight gain (requiring hospitalization in some cases) have been reported in infants who have been human milk-fed by mothers using lamotrigine; whether or not these events were caused by lamotrigine is unknown. No data are available on the effects of the drug on milk production.

The developmental and health benefits of breastfeeding should be considered along with the mother’s clinical need for LAMICTAL and any potential adverse effects on the breastfed infant from LAMICTAL or from the underlying maternal condition.

Clinical Considerations

Human milk-fed infants should be closely monitored for adverse events resulting from lamotrigine. Measurement of infant serum levels should be performed to rule out toxicity if concerns arise. Human milk-feeding should be discontinued in infants with lamotrigine toxicity.

Data

Data from multiple small studies indicate that lamotrigine plasma levels in nursing infants have been reported to be as high as 50% of maternal plasma concentrations.

8.4 Pediatric Use

Epilepsy

LAMICTAL is indicated as adjunctive therapy in patients aged 2 years and older for partial-onset seizures, the generalized seizures of Lennox-Gastaut syndrome, and PGTC seizures.

Safety and efficacy of LAMICTAL used as adjunctive treatment for partial-onset seizures were not demonstrated in a small, randomized, double-blind, placebo-controlled withdrawal trial in very young pediatric patients (aged 1 to 24 months). LAMICTAL was associated with an increased risk for infectious adverse reactions (LAMICTAL 37%, placebo 5%), and respiratory adverse reactions (LAMICTAL 26%, placebo 5%). Infectious adverse reactions included bronchiolitis, bronchitis, ear infection, eye infection, otitis externa, pharyngitis, urinary tract infection, and viral infection. Respiratory adverse reactions included nasal congestion, cough, and apnea.

Bipolar Disorder

Safety and efficacy of LAMICTAL for the maintenance treatment of bipolar disorder were not established in a double-blind, randomized withdrawal, placebo-controlled trial that evaluated 301 pediatric patients aged 10 to 17 years with a current manic/hypomanic, depressed, or mixed mood episode as defined by DSM-IV-TR. In the randomized phase of the trial, adverse reactions that occurred in at least 5% of patients taking LAMICTAL (n = 87) and were twice as common compared with patients taking placebo (n = 86) were influenza (LAMICTAL 8%, placebo 2%), oropharyngeal pain (LAMICTAL 8%, placebo 2%), vomiting (LAMICTAL 6%, placebo 2%), contact dermatitis (LAMICTAL 5%, placebo 2%), upper abdominal pain (LAMICTAL 5%, placebo 1%), and suicidal ideation (LAMICTAL 5%, placebo 0%).

Juvenile Animal Data

In a juvenile animal study in which lamotrigine (oral doses of 0, 5, 15, or 30 mg/kg) was administered to young rats from postnatal day 7 to 62, decreased viability and growth were seen at the highest dose tested and long-term neurobehavioral abnormalities (decreased locomotor activity, increased reactivity, and learning deficits in animals tested as adults) were observed at the 2 highest doses. The no-effect dose for adverse developmental effects in juvenile animals is less than the human dose of 400 mg/day on a mg/m^2 basis.

8.5 Geriatric Use

Clinical trials of LAMICTAL for epilepsy and bipolar disorder did not include sufficient numbers of patients aged 65 years and older to determine whether they respond differently from younger patients or exhibit a different safety profile than that of younger patients. In general, dose selection for an elderly patient should be cautious, usually starting at the low end of the dosing range, reflecting the greater frequency of decreased hepatic, renal, or cardiac function and of concomitant disease or other drug therapy.

8.6 Hepatic Impairment

Experience in patients with hepatic impairment is limited. Based on a clinical pharmacology study in 24 subjects with mild, moderate, and severe liver impairment, the following general recommendations can be made. No dosage adjustment is needed in patients with mild liver impairment [see Clinical Pharmacology (12.3)]. Initial, escalation, and maintenance doses should generally be reduced by approximately 25% in patients with moderate and severe liver impairment without ascites and 50% in patients with severe liver impairment with ascites. Escalation and maintenance doses may be adjusted according to clinical response [see Dosage and Administration (2.1)].

8.7 Renal Impairment

Lamotrigine is metabolized mainly by glucuronic acid conjugation, with the majority of the metabolites being recovered in the urine. In a small study comparing a single dose of lamotrigine in subjects with varying degrees of renal impairment with healthy volunteers, the plasma half-life of lamotrigine was approximately twice as long in the subjects with chronic renal failure [see Clinical Pharmacology (12.3)].

Initial doses of LAMICTAL should be based on patients’ AED regimens; reduced maintenance doses may be effective for patients with significant renal impairment. Few patients with severe renal impairment have been evaluated during chronic treatment with lamotrigine. Because there is inadequate experience in this population, LAMICTAL should be used with caution in these patients [see Dosage and Administration (2.1)].

10 OVERDOSAGE

10.1 Human Overdose Experience

Overdoses involving quantities up to 15 g have been reported for LAMICTAL, some of which have been fatal. Overdose has resulted in ataxia, nystagmus, seizures (including tonic-clonic seizures), decreased level of consciousness, coma, and intraventricular conduction delay.

10.2 Management of Overdose

There are no specific antidotes for lamotrigine. Following a suspected overdose, hospitalization of the patient is advised. General supportive care is indicated, including frequent monitoring of vital signs and close observation of the patient. If indicated, emesis should be induced; usual precautions should be taken to protect the airway. It should be kept in mind that immediate-release lamotrigine is rapidly absorbed [see Clinical Pharmacology (12.3)]. It is uncertain whether hemodialysis is an effective means of removing lamotrigine from the blood. In 6 renal failure patients, about 20% of the amount of lamotrigine in the body was removed by hemodialysis during a 4-hour session. A Poison Control Center should be contacted for information on the management of overdosage of LAMICTAL.

11 DESCRIPTION

LAMICTAL (lamotrigine), an AED of the phenyltriazine class, is chemically unrelated to existing AEDs. Lamotrigine’s chemical name is 3,5-diamino-6-(2,3-dichlorophenyl)-as-triazine, its molecular formula is C9H7N5Cl2, and its molecular weight is 256.09. Lamotrigine is a white to pale cream-colored powder and has a pKa of 5.7. Lamotrigine is very slightly soluble in water (0.17 mg/mL at 25°C) and slightly soluble in 0.1 M HCl (4.1 mg/mL at 25°C). The structural formula is:

LAMICTAL tablets are supplied for oral administration as 25-mg (white), 100-mg (peach), 150-mg (cream), and 200-mg (blue) tablets. Each tablet contains the labeled amount of lamotrigine and the following inactive ingredients: lactose; magnesium stearate; microcrystalline cellulose; povidone; sodium starch glycolate; FD&C Yellow No. 6 Lake (100-mg tablet only); ferric oxide, yellow (150-mg tablet only); and FD&C Blue No. 2 Lake (200-mg tablet only).

LAMICTAL tablets for oral suspension are supplied for oral administration. The tablets contain 2 mg (white), 5 mg (white), or 25 mg (white) of lamotrigine and the following inactive ingredients: blackcurrant flavor, calcium carbonate, low-substituted hydroxypropylcellulose, magnesium aluminum silicate, magnesium stearate, povidone, saccharin sodium, and sodium starch glycolate. The tablets for oral suspension meet Organic Impurities Procedure 2 as published in the current USP monograph for Lamotrigine Tablets for Oral Suspension.

LAMICTAL ODT orally disintegrating tablets are supplied for oral administration. The tablets contain 25 mg (white to off-white), 50 mg (white to off-white), 100 mg (white to off-white), or 200 mg (white to off-white) of lamotrigine and the following inactive ingredients: artificial cherry flavor, crospovidone, ethylcellulose, magnesium stearate, mannitol, polyethylene, and sucralose.

LAMICTAL ODT orally disintegrating tablets are formulated using technologies (Microcaps and AdvaTab) designed to mask the bitter taste of lamotrigine and achieve a rapid dissolution profile. Tablet characteristics including flavor, mouth-feel, after-taste, and ease of use were rated as favorable in a study in 108 healthy volunteers.

12 CLINICAL PHARMACOLOGY

12.1 Mechanism of Action

The precise mechanism(s) by which lamotrigine exerts its anticonvulsant action are unknown. In animal models designed to detect anticonvulsant activity, lamotrigine was effective in preventing seizure spread in the maximum electroshock (MES) and pentylenetetrazol (scMet) tests, and prevented seizures in the visually and electrically evoked after-discharge (EEAD) tests for antiepileptic activity. Lamotrigine also displayed inhibitory properties in the kindling model in rats both during kindling development and in the fully kindled state. The relevance of these models to human epilepsy, however, is not known.

One proposed mechanism of action of lamotrigine, the relevance of which remains to be established in humans, involves an effect on sodium channels. In vitro pharmacological studies suggest that lamotrigine inhibits voltage-sensitive sodium channels, thereby stabilizing neuronal membranes and consequently modulating presynaptic transmitter release of excitatory amino acids (e.g., glutamate and aspartate).

Effect of Lamotrigine on N-Methyl d-Aspartate-Receptor–Mediated Activity

Lamotrigine did not inhibit N-methyl d-aspartate (NMDA)-induced depolarizations in rat cortical slices or NMDA-induced cyclic GMP formation in immature rat cerebellum, nor did lamotrigine displace compounds that are either competitive or noncompetitive ligands at this glutamate receptor complex (CNQX, CGS, TCHP). The IC50 for lamotrigine effects on NMDA-induced currents (in the presence of 3 µM of glycine) in cultured hippocampal neurons exceeded 100 µM.

The mechanisms by which lamotrigine exerts its therapeutic action in bipolar disorder have not been established.

12.2 Pharmacodynamics

Folate Metabolism

In vitro, lamotrigine inhibited dihydrofolate reductase, the enzyme that catalyzes the reduction of dihydrofolate to tetrahydrofolate. Inhibition of this enzyme may interfere with the biosynthesis of nucleic acids and proteins. When oral daily doses of lamotrigine were given to pregnant rats during organogenesis, fetal, placental, and maternal folate concentrations were reduced. Significantly reduced concentrations of folate are associated with teratogenesis [see Use in Specific Populations (8.1)]. Folate concentrations were also reduced in male rats given repeated oral doses of lamotrigine. Reduced concentrations were partially returned to normal when supplemented with folinic acid.

Cardiac Electrophysiology

Effect of Lamotrigine: In vitro studies show that lamotrigine exhibits Class IB antiarrhythmic activity at therapeutically relevant concentrations. It inhibits human cardiac sodium channels with rapid onset and offset kinetics and strong voltage dependence, consistent with other Class IB antiarrhythmic agents. At therapeutic doses, LAMICTAL did not slow ventricular conduction (widen QRS) in healthy individuals in a thorough QT study; however, in patients with clinically important structural or functional heart disease (i.e., patients with heart failure, valvular heart disease, congenital heart disease, conduction system disease, ventricular arrhythmias, cardiac channelopathies [e.g., Brugada syndrome], clinically important ischemic heart disease, or multiple risk factors for coronary artery disease), LAMICTAL could slow ventricular conduction (widen QRS) and induce proarrhythmia, which can lead to sudden death. Elevated heart rates could also increase the risk of ventricular conduction slowing with LAMICTAL.

Effect of Lamotrigine Metabolite: In dogs, lamotrigine is extensively metabolized to a 2-N-methyl metabolite. This metabolite causes dose-dependent prolongation of the PR interval, widening of the QRS complex, and, at higher doses, complete AV conduction block. The in vitro electrophysiological effects of this metabolite have not been studied. Similar cardiovascular effects from this metabolite are not anticipated in humans because only trace amounts of the 2-N-methyl metabolite (<0.6% of lamotrigine dose) have been found in human urine [see Clinical Pharmacology (12.3)]. However, it is conceivable that plasma concentrations of this metabolite could be increased in patients with a reduced capacity to glucuronidate lamotrigine (e.g., in patients with liver disease, patients taking concomitant medications that inhibit glucuronidation).

Accumulation in Kidneys

Lamotrigine accumulated in the kidney of the male rat, causing chronic progressive nephrosis, necrosis, and mineralization. These findings are attributed to α-2 microglobulin, a species- and sex-specific protein that has not been detected in humans or other animal species.

Melanin Binding

Lamotrigine binds to melanin-containing tissues, e.g., in the eye and pigmented skin. It has been found in the uveal tract up to 52 weeks after a single dose in rodents.

12.3 Pharmacokinetics

The pharmacokinetics of lamotrigine have been studied in subjects with epilepsy, healthy young and elderly volunteers, and volunteers with chronic renal failure. Lamotrigine pharmacokinetic parameters for adult and pediatric subjects and healthy normal volunteers are summarized in Tables 14 and 16.

Table 14. Mean Pharmacokinetic Parametersa in Healthy Volunteers and Adult Subjects with Epilepsy
Adult Study Population | Number of Subjects | Tmax: Time of Maximum Plasma Concentration; (h) | t½:; Elimination Half-life; (h) | CL/F:; Apparent Plasma Clearance; (mL/min/kg)
Healthy volunteers taking no other medications:
Single-dose LAMICTAL | 179 | 2.2; (0.25-12.0) | 32.8; (14.0-103.0) | 0.44; (0.12-1.10)
Multiple-dose LAMICTAL | 36 | 1.7; (0.5-4.0) | 25.4; (11.6-61.6) | 0.58; (0.24-1.15)
Healthy volunteers taking valproate:
Single-dose LAMICTAL | 6 | 1.8; (1.0-4.0) | 48.3; (31.5-88.6) | 0.30; (0.14-0.42)
Multiple-dose LAMICTAL | 18 | 1.9; (0.5-3.5) | 70.3; (41.9-113.5) | 0.18; (0.12-0.33)
Subjects with epilepsy taking valproate only:
Single-dose LAMICTAL | 4 | 4.8; (1.8-8.4) | 58.8; (30.5-88.8) | 0.28; (0.16-0.40)
Subjects with epilepsy taking carbamazepine, phenytoin, phenobarbital, or primidoneb plus valproate:
Single-dose LAMICTAL | 25 | 3.8; (1.0-10.0) | 27.2; (11.2-51.6) | 0.53; (0.27-1.04)
Subjects with epilepsy taking carbamazepine, phenytoin, phenobarbital, or primidone:b
Single-dose LAMICTAL | 24 | 2.3; (0.5-5.0) | 14.4; (6.4-30.4) | 1.10; (0.51-2.22)
Multiple-dose LAMICTAL | 17 | 2.0; (0.75-5.93) | 12.6; (7.5-23.1) | 1.21; (0.66-1.82)
a The majority of parameter means determined in each study had coefficients of variation between 20% and 40% for half-life and CL/F and between 30% and 70% for Tmax. The overall mean values were calculated from individual study means that were weighted based on the number of volunteers/subjects in each study. The numbers in parentheses below each parameter mean represent the range of individual volunteer/subject values across studies.
b Carbamazepine, phenytoin, phenobarbital, and primidone have been shown to increase the apparent clearance of lamotrigine. Estrogen-containing oral contraceptives and other drugs, such as rifampin and protease inhibitors lopinavir/ritonavir and atazanavir/ritonavir, that induce lamotrigine glucuronidation have also been shown to increase the apparent clearance of lamotrigine [see Drug Interactions (7)].

Absorption

Lamotrigine is rapidly and completely absorbed after oral administration with negligible first-pass metabolism (absolute bioavailability is 98%). The bioavailability is not affected by food. Peak plasma concentrations occur anywhere from 1.4 to 4.8 hours following drug administration. The lamotrigine tablets for oral suspension were found to be equivalent, whether administered as dispersed in water, chewed and swallowed, or swallowed whole, to the lamotrigine compressed tablets in terms of rate and extent of absorption. In terms of rate and extent of absorption, lamotrigine orally disintegrating tablets, whether disintegrated in the mouth or swallowed whole with water, were equivalent to the lamotrigine compressed tablets swallowed with water.

Dose Proportionality

In healthy volunteers not receiving any other medications and given single doses, the plasma concentrations of lamotrigine increased in direct proportion to the dose administered over the range of 50 to 400 mg. In 2 small studies (n = 7 and 8) of patients with epilepsy who were maintained on other AEDs, there also was a linear relationship between dose and lamotrigine plasma concentrations at steady state following doses of 50 to 350 mg twice daily.

Distribution

Estimates of the mean apparent volume of distribution (Vd/F) of lamotrigine following oral administration ranged from 0.9 to 1.3 L/kg. Vd/F is independent of dose and is similar following single and multiple doses in both patients with epilepsy and in healthy volunteers.

Protein Binding

Data from in vitro studies indicate that lamotrigine is approximately 55% bound to human plasma proteins at plasma lamotrigine concentrations from 1 to 10 mcg/mL (10 mcg/mL is 4 to 6 times the trough plasma concentration observed in the controlled efficacy trials). Because lamotrigine is not highly bound to plasma proteins, clinically significant interactions with other drugs through competition for protein binding sites are unlikely. The binding of lamotrigine to plasma proteins did not change in the presence of therapeutic concentrations of phenytoin, phenobarbital, or valproate. Lamotrigine did not displace other AEDs (carbamazepine, phenytoin, phenobarbital) from protein-binding sites.

Metabolism

Lamotrigine is metabolized predominantly by glucuronic acid conjugation; the major metabolite is an inactive 2-N-glucuronide conjugate. After oral administration of 240 mg of ^14C-lamotrigine (15 μCi) to 6 healthy volunteers, 94% was recovered in the urine and 2% was recovered in the feces. The radioactivity in the urine consisted of unchanged lamotrigine (10%), the 2-N-glucuronide (76%), a 5-N-glucuronide (10%), a 2-N-methyl metabolite (0.14%), and other unidentified minor metabolites (4%).

Enzyme Induction

The effects of lamotrigine on the induction of specific families of mixed-function oxidase isozymes have not been systematically evaluated.

Following multiple administrations (150 mg twice daily) to normal volunteers taking no other medications, lamotrigine induced its own metabolism, resulting in a 25% decrease in t½ and a 37% increase in CL/F at steady state compared with values obtained in the same volunteers following a single dose. Evidence gathered from other sources suggests that self-induction by lamotrigine may not occur when lamotrigine is given as adjunctive therapy in patients receiving enzyme-inducing drugs such as carbamazepine, phenytoin, phenobarbital, primidone, or other drugs such as rifampin and the protease inhibitors lopinavir/ritonavir and atazanavir/ritonavir that induce lamotrigine glucuronidation [see Drug Interactions (7)].

Elimination

The elimination half-life and apparent clearance of lamotrigine following oral administration of LAMICTAL to adult subjects with epilepsy and healthy volunteers is summarized in Table 14. Half-life and apparent oral clearance vary depending on concomitant AEDs.

Drug Interactions

The apparent clearance of lamotrigine is affected by the coadministration of certain medications [see Warnings and Precautions (5.9, 5.12), Drug Interactions (7)].

The net effects of drug interactions with lamotrigine are summarized in Tables 13 and 15, followed by details of the drug interaction studies below.

Table 15. Summary of Drug Interactions with Lamotrigine
Drug | Drug Plasma Concentration with Adjunctive Lamotriginea | Lamotrigine Plasma Concentration with Adjunctive Drugsb
Oral contraceptives (e.g., ethinylestradiol/levonorgestrel)c | ↔d | ↓
Aripiprazole | Not assessed | ↔e
Atazanavir/ritonavir | ↔f | ↓
Bupropion | Not assessed | ↔
Carbamazepine | ↔ | ↓
Carbamazepine epoxideg | ?
Felbamate | Not assessed | ↔
Gabapentin | Not assessed | ↔
Lacosamide | Not assessed | ↔
Levetiracetam | ↔ | ↔
Lithium | ↔ | Not assessed
Lopinavir/ritonavir | ↔e | ↓
Olanzapine | ↔ | ↔e
Oxcarbazepine | ↔ | ↔
10-Monohydroxy oxcarbazepine metaboliteh | ↔
Perampanel | Not assessed | ↔e
Phenobarbital/primidone | ↔ | ↓
Phenytoin | ↔ | ↓
Pregabalin | ↔ | ↔
Rifampin | Not assessed | ↓
Risperidone | ↔ | Not assessed
9-Hydroxyrisperidonei | ↔
Topiramate | ↔j | ↔
Valproate | ↓ | ↑
Valproate + phenytoin and/or carbamazepine | Not assessed | ↔
Zonisamide | Not assessed | ↔
a From adjunctive clinical trials and volunteer trials.
b Net effects were estimated by comparing the mean clearance values obtained in adjunctive clinical trials and volunteer trials.
c The effect of other hormonal contraceptive preparations or hormone replacement therapy on the pharmacokinetics of lamotrigine has not been systematically evaluated in clinical trials, although the effect may be similar to that seen with the ethinylestradiol/levonorgestrel combinations.
d Modest decrease in levonorgestrel.
e Slight decrease, not expected to be clinically meaningful.
f Compared with historical controls.
g Not administered, but an active metabolite of carbamazepine.
h Not administered, but an active metabolite of oxcarbazepine.
i Not administered, but an active metabolite of risperidone.
j Slight increase, not expected to be clinically meaningful.
↔ = No significant effect.
? = Conflicting data.

Estrogen-Containing Oral Contraceptives

In 16 female volunteers, an oral contraceptive preparation containing 30 mcg ethinylestradiol and 150 mcg levonorgestrel increased the apparent clearance of lamotrigine (300 mg/day) by approximately 2-fold with mean decreases in AUC of 52% and in Cmax of 39%. In this study, trough serum lamotrigine concentrations gradually increased and were approximately 2-fold higher on average at the end of the week of the inactive hormone preparation compared with trough lamotrigine concentrations at the end of the active hormone cycle.

Gradual transient increases in lamotrigine plasma levels (approximate 2-fold increase) occurred during the week of inactive hormone preparation (pill-free week) for women not also taking a drug that increased the clearance of lamotrigine (carbamazepine, phenytoin, phenobarbital, primidone, or other drugs such as rifampin and the protease inhibitors lopinavir/ritonavir and atazanavir/ritonavir that induce lamotrigine glucuronidation) [see Drug Interactions (7)]. The increase in lamotrigine plasma levels will be greater if the dose of LAMICTAL is increased in the few days before or during the pill-free week. Increases in lamotrigine plasma levels could result in dose-dependent adverse reactions.

In the same study, coadministration of lamotrigine (300 mg/day) in 16 female volunteers did not affect the pharmacokinetics of the ethinylestradiol component of the oral contraceptive preparation. There were mean decreases in the AUC and Cmax of the levonorgestrel component of 19% and 12%, respectively. Measurement of serum progesterone indicated that there was no hormonal evidence of ovulation in any of the 16 volunteers, although measurement of serum FSH, LH, and estradiol indicated that there was some loss of suppression of the hypothalamic-pituitary-ovarian axis.

The effects of doses of lamotrigine other than 300 mg/day have not been systematically evaluated in controlled clinical trials. Studies with other female hormonal preparations (including progesterone/progesterone-containing HRT) have not been conducted.

The clinical significance of the observed hormonal changes on ovulatory activity is unknown. However, the possibility of decreased contraceptive efficacy in some patients cannot be excluded. Therefore, patients should be instructed to promptly report changes in their menstrual pattern (e.g., break-through bleeding).

Dosage adjustments may be necessary for women receiving estrogen-containing products, including oral contraceptive preparations [see Dosage and Administration (2.1)].

Other Hormonal Contraceptives or Hormone Replacement Therapy

The effect of other hormonal contraceptive preparations or hormone replacement therapy on the pharmacokinetics of lamotrigine has not been systematically evaluated. It has been reported that ethinylestradiol, not progestogens, increased the clearance of lamotrigine up to 2-fold, and the progestin-only pills had no effect on lamotrigine plasma levels. Therefore, adjustments to the dosage of LAMICTAL in the presence of progestogens alone will likely not be needed.

Aripiprazole

In 18 patients with bipolar disorder on a stable regimen of 100 to 400 mg/day of lamotrigine, the lamotrigine AUC and Cmax were reduced by approximately 10% in patients who received aripiprazole 10 to 30 mg/day for 7 days, followed by 30 mg/day for an additional 7 days. This reduction in lamotrigine exposure is not considered clinically meaningful.

Atazanavir/Ritonavir

In a study in healthy volunteers, daily doses of atazanavir/ritonavir (300 mg/100 mg) reduced the plasma AUC and Cmax of lamotrigine (single 100-mg dose) by an average of 32% and 6%, respectively, and shortened the elimination half-lives by 27%. In the presence of atazanavir/ritonavir (300 mg/100 mg), the metabolite-to-lamotrigine ratio was increased from 0.45 to 0.71 consistent with induction of glucuronidation. The pharmacokinetics of atazanavir/ritonavir were similar in the presence of concomitant lamotrigine to the historical data of the pharmacokinetics in the absence of lamotrigine.

Bupropion

The pharmacokinetics of a 100-mg single dose of lamotrigine in healthy volunteers (n = 12) were not changed by coadministration of bupropion sustained-release formulation (150 mg twice daily) starting 11 days before lamotrigine.

Carbamazepine

Lamotrigine has no appreciable effect on steady-state carbamazepine plasma concentration. Limited clinical data suggest there is a higher incidence of dizziness, diplopia, ataxia, and blurred vision in patients receiving carbamazepine with lamotrigine than in patients receiving other AEDs with lamotrigine [see Adverse Reactions (6.1)]. The mechanism of this interaction is unclear. The effect of lamotrigine on plasma concentrations of carbamazepine-epoxide is unclear. In a small subset of patients (n = 7) studied in a placebo-controlled trial, lamotrigine had no effect on carbamazepine-epoxide plasma concentrations, but in a small, uncontrolled study (n = 9), carbamazepine-epoxide levels increased.

The addition of carbamazepine decreases lamotrigine steady-state concentrations by approximately 40%.

Felbamate

In a trial in 21 healthy volunteers, coadministration of felbamate (1,200 mg twice daily) with lamotrigine (100 mg twice daily for 10 days) appeared to have no clinically relevant effects on the pharmacokinetics of lamotrigine.

Folate Inhibitors

Lamotrigine is a weak inhibitor of dihydrofolate reductase. Prescribers should be aware of this action when prescribing other medications that inhibit folate metabolism.

Gabapentin

Based on a retrospective analysis of plasma levels in 34 subjects who received lamotrigine both with and without gabapentin, gabapentin does not appear to change the apparent clearance of lamotrigine.

Lacosamide

Plasma concentrations of lamotrigine were not affected by concomitant lacosamide (200, 400, or 600 mg/day) in placebo-controlled clinical trials in patients with partial-onset seizures.

Levetiracetam

Potential drug interactions between levetiracetam and lamotrigine were assessed by evaluating serum concentrations of both agents during placebo-controlled clinical trials. These data indicate that lamotrigine does not influence the pharmacokinetics of levetiracetam and that levetiracetam does not influence the pharmacokinetics of lamotrigine.

Lithium

The pharmacokinetics of lithium were not altered in healthy subjects (n = 20) by coadministration of lamotrigine (100 mg/day) for 6 days.

Lopinavir/Ritonavir

The addition of lopinavir (400 mg twice daily)/ritonavir (100 mg twice daily) decreased the AUC, Cmax, and elimination half-life of lamotrigine by approximately 50% to 55.4% in 18 healthy subjects. The pharmacokinetics of lopinavir/ritonavir were similar with concomitant lamotrigine, compared with that in historical controls.

Olanzapine

The AUC and Cmax of olanzapine were similar following the addition of olanzapine (15 mg once daily) to lamotrigine (200 mg once daily) in healthy male volunteers (n = 16) compared with the AUC and Cmax in healthy male volunteers receiving olanzapine alone (n = 16).

In the same trial, the AUC and Cmax of lamotrigine were reduced on average by 24% and 20%, respectively, following the addition of olanzapine to lamotrigine in healthy male volunteers compared with those receiving lamotrigine alone. This reduction in lamotrigine plasma concentrations is not expected to be clinically meaningful.

Oxcarbazepine

The AUC and Cmax of oxcarbazepine and its active 10-monohydroxy oxcarbazepine metabolite were not significantly different following the addition of oxcarbazepine (600 mg twice daily) to lamotrigine (200 mg once daily) in healthy male volunteers (n = 13) compared with healthy male volunteers receiving oxcarbazepine alone (n = 13).

In the same trial, the AUC and Cmax of lamotrigine were similar following the addition of oxcarbazepine (600 mg twice daily) to lamotrigine in healthy male volunteers compared with those receiving lamotrigine alone. Limited clinical data suggest a higher incidence of headache, dizziness, nausea, and somnolence with coadministration of lamotrigine and oxcarbazepine compared with lamotrigine alone or oxcarbazepine alone.

Perampanel

In a pooled analysis of data from 3 placebo-controlled clinical trials investigating adjunctive perampanel in patients with partial-onset and PGTC seizures, the highest perampanel dose evaluated (12 mg/day) increased lamotrigine clearance by <10%. An effect of this magnitude is not considered to be clinically relevant.

Phenobarbital, Primidone

The addition of phenobarbital or primidone decreases lamotrigine steady-state concentrations by approximately 40%.

Phenytoin

Lamotrigine has no appreciable effect on steady-state phenytoin plasma concentrations in patients with epilepsy. The addition of phenytoin decreases lamotrigine steady-state concentrations by approximately 40%.

Pregabalin

Steady-state trough plasma concentrations of lamotrigine were not affected by concomitant pregabalin (200 mg 3 times daily) administration. There are no pharmacokinetic interactions between lamotrigine and pregabalin.

Rifampin

In 10 male volunteers, rifampin (600 mg/day for 5 days) significantly increased the apparent clearance of a single 25-mg dose of lamotrigine by approximately 2-fold (AUC decreased by approximately 40%).

Risperidone

In a 14 healthy volunteers study, multiple oral doses of lamotrigine 400 mg daily had no clinically significant effect on the single-dose pharmacokinetics of risperidone 2 mg and its active metabolite 9-OH risperidone. Following the coadministration of risperidone 2 mg with lamotrigine, 12 of the 14 volunteers reported somnolence compared with 1 out of 20 when risperidone was given alone, and none when lamotrigine was administered alone.

Topiramate

Topiramate resulted in no change in plasma concentrations of lamotrigine. Administration of lamotrigine resulted in a 15% increase in topiramate concentrations.

Valproate

When lamotrigine was administered to healthy volunteers (n = 18) receiving valproate, the trough steady-state valproate plasma concentrations decreased by an average of 25% over a 3-week period, and then stabilized. However, adding lamotrigine to the existing therapy did not cause a change in valproate plasma concentrations in either adult or pediatric patients in controlled clinical trials.

The addition of valproate increased lamotrigine steady-state concentrations in normal volunteers by slightly more than 2‑fold. In 1 trial, maximal inhibition of lamotrigine clearance was reached at valproate doses between 250 and 500 mg/day and did not increase as the valproate dose was further increased.

Zonisamide

In a study in 18 patients with epilepsy, coadministration of zonisamide (200 to 400 mg/day) with lamotrigine (150 to 500 mg/day for 35 days) had no significant effect on the pharmacokinetics of lamotrigine.

Known Inducers or Inhibitors of Glucuronidation

Drugs other than those listed above have not been systematically evaluated in combination with lamotrigine. Since lamotrigine is metabolized predominately by glucuronic acid conjugation, drugs that are known to induce or inhibit glucuronidation may affect the apparent clearance of lamotrigine and doses of lamotrigine may require adjustment based on clinical response.

Other

In vitro assessment of the inhibitory effect of lamotrigine at OCT2 demonstrate that lamotrigine, but not the N(2)-glucuronide metabolite, is an inhibitor of OCT2 at potentially clinically relevant concentrations, with IC50 value of 53.8 µM [see Drug Interactions (7)].

Results of in vitro experiments suggest that clearance of lamotrigine is unlikely to be reduced by concomitant administration of amitriptyline, clonazepam, clozapine, fluoxetine, haloperidol, lorazepam, phenelzine, sertraline, or trazodone.

Results of in vitro experiments suggest that lamotrigine does not reduce the clearance of drugs eliminated predominantly by CYP2D6.

Specific Populations

Patients with Renal Impairment: Twelve volunteers with chronic renal failure (mean creatinine clearance: 13 mL/min, range: 6 to 23) and another 6 individuals undergoing hemodialysis were each given a single 100-mg dose of lamotrigine. The mean plasma half-lives determined in the study were 42.9 hours (chronic renal failure), 13.0 hours (during hemodialysis), and 57.4 hours (between hemodialysis) compared with 26.2 hours in healthy volunteers. On average, approximately 20% (range: 5.6 to 35.1) of the amount of lamotrigine present in the body was eliminated by hemodialysis during a 4-hour session [see Dosage and Administration (2.1)].

Patients with Hepatic Impairment: The pharmacokinetics of lamotrigine following a single 100-mg dose of lamotrigine were evaluated in 24 subjects with mild, moderate, and severe hepatic impairment (Child-Pugh classification system) and compared with 12 subjects without hepatic impairment. The subjects with severe hepatic impairment were without ascites (n = 2) or with ascites (n = 5). The mean apparent clearances of lamotrigine in subjects with mild (n = 12), moderate (n = 5), severe without ascites (n = 2), and severe with ascites (n = 5) liver impairment were 0.30 ± 0.09, 0.24 ± 0.1, 0.21 ± 0.04, and 0.15 ± 0.09 mL/min/kg, respectively, as compared with 0.37 ± 0.1 mL/min/kg in the healthy controls. Mean half-lives of lamotrigine in subjects with mild, moderate, severe without ascites, and severe with ascites hepatic impairment were 46 ± 20, 72 ± 44, 67 ± 11, and 100 ± 48 hours, respectively, as compared with 33 ± 7 hours in healthy controls [see Dosage and Administration (2.1)].

Pediatric Patients: The pharmacokinetics of lamotrigine following a single 2-mg/kg dose were evaluated in 2 studies in pediatric subjects (n = 29 for subjects aged 10 months to 5.9 years and n = 26 for subjects aged 5 to 11 years). Forty-three subjects received concomitant therapy with other AEDs and 12 subjects received lamotrigine as monotherapy. Lamotrigine pharmacokinetic parameters for pediatric patients are summarized in Table 16.

Population pharmacokinetic analyses involving subjects aged 2 to 18 years demonstrated that lamotrigine clearance was influenced predominantly by total body weight and concurrent AED therapy. The oral clearance of lamotrigine was higher, on a body weight basis, in pediatric patients than in adults. Weight-normalized lamotrigine clearance was higher in those subjects weighing <30 kg compared with those weighing >30 kg. Accordingly, patients weighing <30 kg may need an increase of as much as 50% in maintenance doses, based on clinical response, as compared with subjects weighing >30 kg being administered the same AEDs [see Dosage and Administration (2.2)]. These analyses also revealed that, after accounting for body weight, lamotrigine clearance was not significantly influenced by age. Thus, the same weight-adjusted doses should be administered to children irrespective of differences in age. Concomitant AEDs which influence lamotrigine clearance in adults were found to have similar effects in children.

Table 16. Mean Pharmacokinetic Parameters in Pediatric Subjects with Epilepsy
Pediatric Study Population | Number of Subjects | Tmax; (h) | t½; (h) | CL/F; (mL/min/kg)
Ages 10 months-5.3 years
Subjects taking carbamazepine, phenytoin, phenobarbital, or primidonea | 10 | 3.0; (1.0-5.9) | 7.7; (5.7-11.4) | 3.62; (2.44-5.28)
Subjects taking antiepileptic drugs with no known effect on the apparent clearance of lamotrigine | 7 | 5.2; (2.9-6.1) | 19.0; (12.9-27.1) | 1.2; (0.75-2.42)
Subjects taking valproate only | 8 | 2.9; (1.0-6.0) | 44.9; (29.5-52.5) | 0.47; (0.23-0.77)
Ages 5-11 years
Subjects taking carbamazepine, phenytoin, phenobarbital, or primidonea | 7 | 1.6; (1.0-3.0) | 7.0; (3.8-9.8) | 2.54; (1.35-5.58)
Subjects taking carbamazepine, phenytoin, phenobarbital, or primidonea plus valproate | 8 | 3.3; (1.0-6.4) | 19.1; (7.0-31.2) | 0.89; (0.39-1.93)
Subjects taking valproate onlyb | 3 | 4.5; (3.0-6.0) | 65.8; (50.7-73.7) | 0.24; (0.21-0.26)
Ages 13-18 years
Subjects taking carbamazepine, phenytoin, phenobarbital, or primidonea | 11 | ___c | ___c | 1.3
Subjects taking carbamazepine, phenytoin, phenobarbital, or primidonea plus valproate | 8 | ___c | ___c | 0.5
Subjects taking valproate only | 4 | ___c | ___c | 0.3
a Carbamazepine, phenytoin, phenobarbital, and primidone have been shown to increase the apparent clearance of lamotrigine. Estrogen-containing oral contraceptives, rifampin, and the protease inhibitors lopinavir/ritonavir and atazanavir/ritonavir have also been shown to increase the apparent clearance of lamotrigine [see Drug Interactions (7)].
b Two subjects were included in the calculation for mean Tmax.
c Parameter not estimated.

Geriatric Patients: The pharmacokinetics of lamotrigine following a single 150-mg dose of lamotrigine were evaluated in 12 elderly volunteers between the ages of 65 and 76 years (mean creatinine clearance = 61 mL/min, range: 33 to 108 mL/min). The mean half-life of lamotrigine in these subjects was 31.2 hours (range: 24.5 to 43.4 hours), and the mean clearance was 0.40 mL/min/kg (range: 0.26 to 0.48 mL/min/kg).

Male and Female Patients: The clearance of lamotrigine is not affected by gender. However, during dose escalation of lamotrigine in 1 clinical trial in patients with epilepsy on a stable dose of valproate (n = 77), mean trough lamotrigine concentrations unadjusted for weight were 24% to 45% higher (0.3 to 1.7 mcg/mL) in females than in males.

Racial or Ethnic Groups: The apparent oral clearance of lamotrigine was 25% lower in non-Caucasians than Caucasians.

13 NONCLINICAL TOXICOLOGY

13.1 Carcinogenesis, Mutagenesis, Impairment of Fertility

No evidence of carcinogenicity was seen in mice or rats following oral administration of lamotrigine for up to 2 years at doses up to 30 mg/kg/day and 10 to 15 mg/kg/day, respectively. The highest doses tested are less than the human dose of 400 mg/day on a body surface area (mg/m^2) basis.

Lamotrigine was negative in in vitro gene mutation (Ames and mouse lymphoma tk) assays and in clastogenicity (in vitro human lymphocyte and in vivo rat bone marrow) assays.

No evidence of impaired fertility was detected in rats given oral doses of lamotrigine up to 20 mg/kg/day. The highest dose tested is less than the human dose of 400 mg/day on a mg/m^2 basis.

14 CLINICAL STUDIES

14.1 Epilepsy

Monotherapy with LAMICTAL in Adults with Partial-Onset Seizures Already Receiving Treatment with Carbamazepine, Phenytoin, Phenobarbital, or Primidone as the Single Antiepileptic Drug

The effectiveness of monotherapy with LAMICTAL was established in a multicenter, double-blind clinical trial enrolling 156 adult outpatients with partial-onset seizures. The patients experienced at least 4 simple partial-onset, complex partial‑onset, and/or secondarily generalized seizures during each of 2 consecutive 4-week periods while receiving carbamazepine or phenytoin monotherapy during baseline. LAMICTAL (target dose of 500 mg/day) or valproate (1,000 mg/day) was added to either carbamazepine or phenytoin monotherapy over a 4-week period. Patients were then converted to monotherapy with LAMICTAL or valproate during the next 4 weeks, then continued on monotherapy for an additional 12-week period.

Trial endpoints were completion of all weeks of trial treatment or meeting an escape criterion. Criteria for escape relative to baseline were: (1) doubling of average monthly seizure count, (2) doubling of highest consecutive 2-day seizure frequency, (3) emergence of a new seizure type (defined as a seizure that did not occur during the 8-week baseline) that is more severe than seizure types that occur during study treatment, or (4) clinically significant prolongation of generalized tonic-clonic seizures. The primary efficacy variable was the proportion of patients in each treatment group who met escape criteria.

The percentages of patients who met escape criteria were 42% (32/76) in the group receiving LAMICTAL and 69% (55/80) in the valproate group. The difference in the percentage of patients meeting escape criteria was statistically significant (P = 0.0012) in favor of LAMICTAL. No differences in efficacy based on age, sex, or race were detected.

Patients in the control group were intentionally treated with a relatively low dose of valproate; as such, the sole objective of this trial was to demonstrate the effectiveness and safety of monotherapy with LAMICTAL, and cannot be interpreted to imply the superiority of LAMICTAL to an adequate dose of valproate.

Adjunctive Therapy with LAMICTAL in Adults with Partial-Onset Seizures

The effectiveness of LAMICTAL as adjunctive therapy (added to other AEDs) was initially established in 3 pivotal, multicenter, placebo-controlled, double-blind clinical trials in 355 adults with refractory partial-onset seizures. The patients had a history of at least 4 partial-onset seizures per month in spite of receiving 1 or more AEDs at therapeutic concentrations and in 2 of the trials were observed on their established AED regimen during baselines that varied between 8 to 12 weeks. In the third trial, patients were not observed in a prospective baseline. In patients continuing to have at least 4 seizures per month during the baseline, LAMICTAL or placebo was then added to the existing therapy. In all 3 trials, change from baseline in seizure frequency was the primary measure of effectiveness. The results given below are for all partial-onset seizures in the intent-to-treat population (all patients who received at least 1 dose of treatment) in each trial, unless otherwise indicated. The median seizure frequency at baseline was 3 per week while the mean at baseline was 6.6 per week for all patients enrolled in efficacy trials.

One trial (n = 216) was a double-blind, placebo-controlled, parallel trial consisting of a 24-week treatment period. Patients could not be on more than 2 other anticonvulsants and valproate was not allowed. Patients were randomized to receive placebo, a target dose of 300 mg/day of LAMICTAL, or a target dose of 500 mg/day of LAMICTAL. The median reductions in the frequency of all partial-onset seizures relative to baseline were 8% in patients receiving placebo, 20% in patients receiving 300 mg/day of LAMICTAL, and 36% in patients receiving 500 mg/day of LAMICTAL. The seizure frequency reduction was statistically significant in the 500-mg/day group compared with the placebo group, but not in the 300-mg/day group.

A second trial (n = 98) was a double-blind, placebo-controlled, randomized, crossover trial consisting of two 14-week treatment periods (the last 2 weeks of which consisted of dose tapering) separated by a 4-week washout period. Patients could not be on more than 2 other anticonvulsants and valproate was not allowed. The target dose of LAMICTAL was 400 mg/day. When the first 12 weeks of the treatment periods were analyzed, the median change in seizure frequency was a 25% reduction on LAMICTAL compared with placebo (P<0.001).

The third trial (n = 41) was a double-blind, placebo-controlled, crossover trial consisting of two 12-week treatment periods separated by a 4-week washout period. Patients could not be on more than 2 other anticonvulsants. Thirteen patients were on concomitant valproate; these patients received 150 mg/day of LAMICTAL. The 28 other patients had a target dose of 300 mg/day of LAMICTAL. The median change in seizure frequency was a 26% reduction on LAMICTAL compared with placebo (P<0.01).

No differences in efficacy based on age, sex, or race, as measured by change in seizure frequency, were detected.

Adjunctive Therapy with LAMICTAL in Pediatric Patients with Partial-Onset Seizures

The effectiveness of LAMICTAL as adjunctive therapy in pediatric patients with partial-onset seizures was established in a multicenter, double-blind, placebo-controlled trial in 199 patients aged 2 to 16 years (n = 98 on LAMICTAL, n = 101 on placebo). Following an 8-week baseline phase, patients were randomized to 18 weeks of treatment with LAMICTAL or placebo added to their current AED regimen of up to 2 drugs. Patients were dosed based on body weight and valproate use. Target doses were designed to approximate 5 mg/kg/day for patients taking valproate (maximum dose: 250 mg/day) and 15 mg/kg/day for the patients not taking valproate (maximum dose: 750 mg/day). The primary efficacy endpoint was percentage change from baseline in all partial-onset seizures. For the intent-to-treat population, the median reduction of all partial-onset seizures was 36% in patients treated with LAMICTAL and 7% on placebo, a difference that was statistically significant (P<0.01).

Adjunctive Therapy with LAMICTAL in Pediatric and Adult Patients with Lennox-Gastaut Syndrome

The effectiveness of LAMICTAL as adjunctive therapy in patients with Lennox-Gastaut syndrome was established in a multicenter, double-blind, placebo-controlled trial in 169 patients aged 3 to 25 years (n = 79 on LAMICTAL, n = 90 on placebo). Following a 4-week, single-blind, placebo phase, patients were randomized to 16 weeks of treatment with LAMICTAL or placebo added to their current AED regimen of up to 3 drugs. Patients were dosed on a fixed-dose regimen based on body weight and valproate use. Target doses were designed to approximate 5 mg/kg/day for patients taking valproate (maximum dose: 200 mg/day) and 15 mg/kg/day for patients not taking valproate (maximum dose: 400 mg/day). The primary efficacy endpoint was percentage change from baseline in major motor seizures (atonic, tonic, major myoclonic, and tonic-clonic seizures). For the intent-to-treat population, the median reduction of major motor seizures was 32% in patients treated with LAMICTAL and 9% on placebo, a difference that was statistically significant (P<0.05). Drop attacks were significantly reduced by LAMICTAL (34%) compared with placebo (9%), as were tonic-clonic seizures (36% reduction versus 10% increase for LAMICTAL and placebo, respectively).

Adjunctive Therapy with LAMICTAL in Pediatric and Adult Patients with Primary Generalized Tonic-Clonic Seizures

The effectiveness of LAMICTAL as adjunctive therapy in patients with PGTC seizures was established in a multicenter, double-blind, placebo-controlled trial in 117 pediatric and adult patients aged 2 years and older (n = 58 on LAMICTAL, n = 59 on placebo). Patients with at least 3 PGTC seizures during an 8-week baseline phase were randomized to 19 to 24 weeks of treatment with LAMICTAL or placebo added to their current AED regimen of up to 2 drugs. Patients were dosed on a fixed-dose regimen, with target doses ranging from 3 to 12 mg/kg/day for pediatric patients and from 200 to 400 mg/day for adult patients based on concomitant AEDs.

The primary efficacy endpoint was percentage change from baseline in PGTC seizures. For the intent-to-treat population, the median percent reduction in PGTC seizures was 66% in patients treated with LAMICTAL and 34% on placebo, a difference that was statistically significant (P = 0.006).

14.2 Bipolar Disorder

Adults

The effectiveness of LAMICTAL in the maintenance treatment of bipolar I disorder was established in 2 multicenter, double-blind, placebo-controlled trials in adult patients (aged 18 to 82 years) who met DSM-IV criteria for bipolar I disorder. Trial 1 enrolled patients with a current or recent (within 60 days) depressive episode as defined by DSM-IV and Trial 2 included patients with a current or recent (within 60 days) episode of mania or hypomania as defined by DSM-IV. Both trials included a cohort of patients (30% of 404 subjects in Trial 1 and 28% of 171 patients in Trial 2) with rapid cycling bipolar disorder (4 to 6 episodes per year).

In both trials, patients were titrated to a target dose of 200 mg of LAMICTAL as add-on therapy or as monotherapy with gradual withdrawal of any psychotropic medications during an 8- to 16-week open-label period. Overall 81% of 1,305 patients participating in the open-label period were receiving 1 or more other psychotropic medications, including benzodiazepines, selective serotonin reuptake inhibitors (SSRIs), atypical antipsychotics (including olanzapine), valproate, or lithium, during titration of LAMICTAL. Patients with a CGI-severity score of 3 or less maintained for at least 4 continuous weeks, including at least the final week on monotherapy with LAMICTAL, were randomized to a placebo-controlled double-blind treatment period for up to 18 months. The primary endpoint was TIME (time to intervention for a mood episode or one that was emerging, time to discontinuation for either an adverse event that was judged to be related to bipolar disorder, or for lack of efficacy). The mood episode could be depression, mania, hypomania, or a mixed episode.

In Trial 1, patients received double-blind monotherapy with LAMICTAL 50 mg/day (n = 50), LAMICTAL 200 mg/day (n = 124), LAMICTAL 400 mg/day (n = 47), or placebo (n = 121). LAMICTAL (200- and 400-mg/day treatment groups combined) was superior to placebo in delaying the time to occurrence of a mood episode (Figure 1). Separate analyses of the 200- and 400-mg/day dose groups revealed no added benefit from the higher dose.

In Trial 2, patients received double-blind monotherapy with LAMICTAL (100 to 400 mg/day, n = 59), or placebo (n = 70). LAMICTAL was superior to placebo in delaying time to occurrence of a mood episode (Figure 2). The mean dose of LAMICTAL was about 211 mg/day.

Although these trials were not designed to separately evaluate time to the occurrence of depression or mania, a combined analysis for the 2 trials revealed a statistically significant benefit for LAMICTAL over placebo in delaying the time to occurrence of both depression and mania, although the finding was more robust for depression.

Figure 1: Kaplan-Meier Estimation of Cumulative Proportion of Patients with Mood Episode (Trial 1)

Figure 2: Kaplan-Meier Estimation of Cumulative Proportion of Patients with Mood Episode (Trial 2)

16 HOW SUPPLIED/STORAGE AND HANDLING

LAMICTAL (lamotrigine) tablets

25-mg, white, scored, shield-shaped tablets debossed with “LAMICTAL” and “25”, bottles of 100 (NDC 0173-0633-02).

Store at 25°C (77°F); excursions permitted to 15°C to 30°C (59°F to 86°F) [see USP Controlled Room Temperature] in a dry place.

100-mg, peach, scored, shield-shaped tablets debossed with “LAMICTAL” and “100”, bottles of 100 (NDC 0173-0642-55).

150-mg, cream, scored, shield-shaped tablets debossed with “LAMICTAL” and “150”, bottles of 60 (NDC 0173-0643-60).

200-mg, blue, scored, shield-shaped tablets debossed with “LAMICTAL” and “200”, bottles of 60 (NDC 0173-0644-60).

Store at 25°C (77°F); excursions permitted to 15°C to 30°C (59°F to 86°F) [see USP Controlled Room Temperature] in a dry place and protect from light.

LAMICTAL (lamotrigine) Starter Kit for Patients Taking Valproate (Blue Kit)

25-mg, white, scored, shield-shaped tablets debossed with “LAMICTAL” and “25”, blister pack of 35 tablets (NDC 0173-0633-10).

Store at 25°C (77°F); excursions permitted to 15°C to 30°C (59°F to 86°F) [see USP Controlled Room Temperature] in a dry place.

LAMICTAL (lamotrigine) Starter Kit for Patients Taking Carbamazepine, Phenytoin, Phenobarbital, or Primidone and Not Taking Valproate (Green Kit)

25-mg, white, scored, shield-shaped tablets debossed with “LAMICTAL” and “25” and 100 mg, peach, scored, shield-shaped tablets debossed with “LAMICTAL” and “100”, blister pack of 98 tablets (84/25-mg tablets and 14/100-mg tablets) (NDC 0173-0817-28).

Store at 25°C (77°F); excursions permitted to 15°C to 30°C (59°F to 86°F) [see USP Controlled Room Temperature] in a dry place and protect from light.

LAMICTAL (lamotrigine) Starter Kit for Patients Not Taking Carbamazepine, Phenytoin, Phenobarbital, Primidone, or Valproate (Orange Kit)

25-mg, white, scored, shield-shaped tablets debossed with “LAMICTAL” and “25” and 100 mg, peach, scored, shield-shaped tablets debossed with “LAMICTAL” and “100”, blister pack of 49 tablets (42/25-mg tablets and 7/100-mg tablets) (NDC 0173-0594-02).

Store at 25°C (77°F); excursions permitted to 15°C to 30°C (59°F to 86°F) [see USP Controlled Room Temperature] in a dry place and protect from light.

LAMICTAL (lamotrigine) tablets for oral suspension

2-mg, white to off-white, round tablets debossed with “LTG” over “2”, bottles of 30 (NDC 0173-0699-00). ORDER DIRECTLY FROM GlaxoSmithKline 1-800-334-4153.

5-mg, white to off-white, caplet-shaped tablets debossed with “GX CL2”, bottles of 100 (NDC 0173-0526-00).

25-mg, white, super elliptical-shaped tablets debossed with “GX CL5”, bottles of 100 (NDC 0173-0527-00).

Store at 25°C (77°F); excursions permitted to 15°C to 30°C (59°F to 86°F) [see USP Controlled Room Temperature] in a dry place.

LAMICTAL ODT (lamotrigine) orally disintegrating tablets

25-mg, white to off-white, round, flat-faced, radius-edged tablets debossed with “LMT” on one side and “25” on the other, Maintenance Packs of 30 (NDC 0173-0772-02).

50-mg, white to off-white, round, flat-faced, radius-edged tablets debossed with “LMT” on one side and “50” on the other, Maintenance Packs of 30 (NDC 0173-0774-02).

100-mg, white to off-white, round, flat-faced, radius-edged tablets debossed with “LAMICTAL” on one side and “100” on the other, Maintenance Packs of 30 (NDC 0173-0776-02).

200-mg, white to off-white, round, flat-faced, radius-edged tablets debossed with “LAMICTAL” on one side and “200” on the other, Maintenance Packs of 30 (NDC 0173-0777-02).

Store between 20°C and 25°C (68°F and 77°F); with excursions permitted between 15°C and 30°C (59°F and 86°F).

LAMICTAL ODT (lamotrigine) Patient Titration Kit for Patients Taking Valproate (Blue ODT Kit)

25-mg, white to off-white, round, flat-faced, radius-edged tablets debossed with “LMT” on one side and “25” on the other, and 50 mg, white to off-white, round, flat-faced, radius-edged tablets debossed with “LMT” on one side and “50” on the other, blister pack of 28 tablets (21/25-mg tablets and 7/50-mg tablets) (NDC 0173-0779-00).

Store between 20°C and 25°C (68°F and 77°F); with excursions permitted between 15°C and 30°C (59°F and 86°F).

LAMICTAL ODT (lamotrigine) Patient Titration Kit for Patients Taking Carbamazepine, Phenytoin, Phenobarbital, or Primidone and Not Taking Valproate (Green ODT Kit)

50-mg, white to off-white, round, flat-faced, radius-edged tablets debossed with “LMT” on one side and “50” on the other, and 100 mg, white to off-white, round, flat-faced, radius-edged tablets debossed with “LAMICTAL” on one side and “100” on the other, blister pack of 56 tablets (42/50-mg tablets and 14/100-mg tablets) (NDC 0173-0780-00).

Store between 20°C and 25°C (68°F and 77°F); with excursions permitted between 15°C and 30°C (59°F and 86°F).

LAMICTAL ODT (lamotrigine) Patient Titration Kit for Patients Not Taking Carbamazepine, Phenytoin, Phenobarbital, Primidone, or Valproate (Orange ODT Kit)

25-mg, white to off-white, round, flat-faced, radius-edged tablets debossed with “LMT” on one side and “25” on the other, 50 mg, white to off-white, round, flat-faced, radius-edged tablets debossed with “LMT” on one side and “50” on the other, and 100 mg, white to off-white, round, flat-faced, radius-edged tablets debossed with “LAMICTAL” on one side and “100” on the other, blister pack of 35 (14/25-mg tablets, 14/50-mg tablets, and 7/100-mg tablets) (NDC 0173-0778-00).

Store between 20°C and 25°C (68°F and 77°F); with excursions permitted between 15°C and 30°C (59°F and 86°F).

Blister Packs

If the product is dispensed in a blister pack, the patient should be advised to examine the blister pack before use and not use if blisters are torn, broken, or missing.

17 PATIENT COUNSELING INFORMATION

Advise the patient to read the FDA-approved patient labeling (Medication Guide).

Rash

Prior to initiation of treatment with LAMICTAL, inform patients that a rash or other signs or symptoms of hypersensitivity (e.g., fever, lymphadenopathy) may herald a serious medical event and instruct them to report any such occurrence to their healthcare providers immediately.

Hemophagocytic Lymphohistiocytosis

Prior to initiation of treatment with LAMICTAL, inform patients that excessive immune activation may occur with LAMICTAL and that they should report signs or symptoms such as fever, rash, or lymphadenopathy to a healthcare provider immediately.

Multiorgan Hypersensitivity Reactions, Blood Dyscrasias, and Organ Failure

Inform patients that multiorgan hypersensitivity reactions and acute multiorgan failure may occur with LAMICTAL. Isolated organ failure or isolated blood dyscrasias without evidence of multiorgan hypersensitivity may also occur. Instruct patients to contact their healthcare providers immediately if they experience any signs or symptoms of these conditions [see Warnings and Precautions (5.3, 5.5)].

Cardiac Rhythm and Conduction Abnormalities

Inform patients that, due to its mechanism of action, LAMICTAL could lead to irregular or slowed heart rhythm. This risk is increased in patients with underlying cardiac disease or heart conduction problems or who are taking other medications that affect heart conduction. Patients should be made aware of and report cardiac signs or symptoms to their healthcare provider right away. Patients who develop syncope should lie down with raised legs and contact their healthcare provider [see Warnings and Precautions (5.4)].

Suicidal Thinking and Behavior

Inform patients, their caregivers, and families that AEDs, including LAMICTAL, may increase the risk of suicidal thoughts and behavior. Instruct them to be alert for the emergence or worsening of symptoms of depression, any unusual changes in mood or behavior, or the emergence of suicidal thoughts or behavior or thoughts about self-harm. Instruct them to immediately report behaviors of concern to their healthcare providers.

Worsening of Seizures

Instruct patients to notify their healthcare providers if worsening of seizure control occurs.

Central Nervous System Adverse Effects

Inform patients that LAMICTAL may cause dizziness, somnolence, and other symptoms and signs of central nervous system depression. Accordingly, instruct them neither to drive a car nor to operate other complex machinery until they have gained sufficient experience on LAMICTAL to gauge whether or not it adversely affects their mental and/or motor performance.

Pregnancy and Nursing

Instruct patients to notify their healthcare providers if they become pregnant or intend to become pregnant during therapy and if they intend to breastfeed or are breastfeeding an infant.

Encourage patients to enroll in the NAAED Pregnancy Registry if they become pregnant. This registry is collecting information about the safety of AEDs during pregnancy. To enroll, patients can call the toll-free number 1-888-233-2334 [see Use in Specific Populations (8.1)].

Inform patients who intend to breastfeed that LAMICTAL is present in breast milk and advise them to monitor their child for potential adverse effects of this drug. Discuss the benefits and risks of continuing breastfeeding.

Use of Estrogen-Containing Products, Including Oral Contraceptives

Instruct women to notify their healthcare providers if they plan to start or stop use of oral contraceptives or other female hormonal preparations (including HRT). Starting estrogen-containing products, including oral contraceptives, may significantly decrease lamotrigine plasma levels, and stopping estrogen-containing oral contraceptives (including the pill-free week) may significantly increase lamotrigine plasma levels [see Warnings and Precautions (5.9), Clinical Pharmacology (12.3)]. Also instruct women to promptly notify their healthcare providers if they experience adverse reactions or changes in menstrual pattern (e.g., break-through bleeding) while receiving LAMICTAL in combination with these medications.

Discontinuing LAMICTAL

Instruct patients to notify their healthcare providers if they stop taking LAMICTAL for any reason and not to resume LAMICTAL without consulting their healthcare providers.

Aseptic Meningitis

Inform patients that LAMICTAL may cause aseptic meningitis. Instruct them to notify their healthcare providers immediately if they develop signs and symptoms of meningitis such as headache, fever, nausea, vomiting, stiff neck, rash, abnormal sensitivity to light, myalgia, chills, confusion, or drowsiness while taking LAMICTAL.

Potential Medication Errors

To avoid a medication error of using the wrong drug or formulation, strongly advise patients to visually inspect their tablets to verify that they are LAMICTAL, as well as the correct formulation of LAMICTAL, each time they fill their prescription [see Dosage Forms and Strengths (3.1, 3.2, 3.3), How Supplied/Storage and Handling (16)]. Refer the patient to the Medication Guide that provides depictions of the LAMICTAL tablets, tablets for oral suspension, and orally disintegrating tablets.

LAMICTAL and LAMICTAL ODT are trademarks owned by or licensed to the GSK group of companies. The other brands listed are trademarks owned by or licensed to their respective owners and are not owned by or licensed to the GSK group of companies. The makers of these brands are not affiliated with and do not endorse the GSK group of companies or its products.

Distributed by

GlaxoSmithKline

Durham, NC 27701

©2025 GSK group of companies or its licensor.

LMT:28PI

MEDICATION GUIDE

LAMICTAL (la-MIK-tal) (lamotrigine) tablets

LAMICTAL (lamotrigine) tablets for oral suspension

LAMICTAL ODT (lamotrigine) orally disintegrating tablets

What is the most important information I should know about LAMICTAL?

1. LAMICTAL may cause a serious skin rash that may cause you to be hospitalized or even cause death.
  There is no way to tell if a mild rash will become more serious. A serious skin rash can happen at any time during your treatment with LAMICTAL, but is more likely to happen within the first 2 to 8 weeks of treatment. Children and teenagers aged between 2 and 17 years have a higher chance of getting this serious skin rash while taking LAMICTAL.
  The risk of getting a serious skin rash is higher if you:
  1. take LAMICTAL while taking valproate [DEPAKENE (valproic acid) or DEPAKOTE (divalproex sodium)].
  2. take a higher starting dose of LAMICTAL than your healthcare provider prescribed.
  3. increase your dose of LAMICTAL faster than prescribed.
    The risk of serious skin reactions may be associated with a variant in genes called HLA B*1502 in people from Asian origin (mainly of Han Chinese and Thai origin). See, “Before taking LAMICTAL, tell your healthcare provider about all of your health conditions”.
Call your healthcare provider right away if you have any of the following:
  4. a skin rash
  5. blistering or peeling of your skin
  6. hives
  7. painful sores in your mouth or around your eyes
These symptoms may be the first signs of a serious skin reaction. A healthcare provider should examine you to decide if you should continue taking LAMICTAL.
2. Other serious reactions, including serious blood problems or liver problems. LAMICTAL can also cause other types of allergic reactions or serious problems that may affect organs and other parts of your body like your liver or blood cells. You may or may not have a rash with these types of reactions. Call your healthcare provider right away if you have any of these symptoms:
  1. fever
  2. frequent infections
  3. severe muscle pain
  4. swelling of your face, eyes, lips, or tongue
  5. swollen lymph glands
  6. unusual bruising or bleeding, looking pale
  7. weakness, fatigue
  8. yellowing of your skin or the white part of your eyes
  9. trouble walking or seeing
  10. seizures for the first time or happening more often
  11. pain and/or tenderness in the area towards the top of your stomach (enlarged liver and/or spleen)
3. In patients with known heart problems, the use of LAMICTAL may lead to a fast heart beat. Call your healthcare provider right away if you:
  1. have a fast, slow, or pounding heart beat.
  2. feel your heart skip a beat.
  3. have shortness of breath.
  4. have chest pain.
  5. feel lightheaded.
4. Like other antiepileptic drugs, LAMICTAL may cause suicidal thoughts or actions in a very small number of people, about 1 in 500.
  Call a healthcare provider right away if you have any of these symptoms, especially if they are new, worse, or worry you:
  1. thoughts about suicide or dying
  2. attempt to commit suicide
  3. new or worse depression
  4. new or worse anxiety
  5. feeling agitated or restless
  6. panic attacks
  7. trouble sleeping (insomnia)
  8. new or worse irritability
  9. acting aggressive, being angry, or violent
  10. acting on dangerous impulses
  11. an extreme increase in activity and talking (mania)
  12. other unusual changes in behavior or mood
Do not stop LAMICTAL without first talking to a healthcare provider.
  13. Stopping LAMICTAL suddenly can cause serious problems.
  14. Suicidal thoughts or actions can be caused by things other than medicines. If you have suicidal thoughts or actions, your healthcare provider may check for other causes.
How can I watch for early symptoms of suicidal thoughts and actions in myself or a family member?
  15. Pay attention to any changes, especially sudden changes, in mood, behaviors, thoughts, or feelings.
  16. Keep all follow-up visits with your healthcare provider as scheduled.
  17. Call your healthcare provider between visits as needed, especially if you are worried about symptoms.
5. LAMICTAL may cause aseptic meningitis, a serious inflammation of the protective membrane that covers the brain and spinal cord.
  Call your healthcare provider right away if you have any of the following symptoms:
  1. headache
  2. fever
  3. nausea
  4. vomiting
  5. stiff neck
  6. rash
  7. unusual sensitivity to light
  8. muscle pains
  9. chills
  10. confusion
  11. drowsiness
Meningitis has many causes other than LAMICTAL, which your doctor would check for if you developed meningitis while taking LAMICTAL.
  LAMICTAL can cause other serious side effects. For more information ask your healthcare provider or pharmacist. Tell your healthcare provider if you have any side effect that bothers you. Be sure to read the section below entitled “What are the possible side effects of LAMICTAL?”
6. People prescribed LAMICTAL have sometimes been given the wrong medicine because many medicines have names similar to LAMICTAL, so always check that you receive LAMICTAL.
  Taking the wrong medication can cause serious health problems. When your healthcare provider gives you a prescription for LAMICTAL:
  1. Make sure you can read it clearly.
  2. Talk to your pharmacist to check that you are given the correct medicine.
  3. Each time you fill your prescription, check the tablets you receive against the pictures of the tablets below.
These pictures show the distinct wording, colors, and shapes of the tablets that help to identify the right strength of LAMICTAL tablets, tablets for oral suspension, and orally disintegrating tablets. Immediately call your pharmacist if you receive a LAMICTAL tablet that does not look like one of the tablets shown below, as you may have received the wrong medication.

LAMICTAL (lamotrigine) tablets

25 mg, white

Imprinted with

LAMICTAL 25

100 mg, peach

Imprinted with

LAMICTAL 100

150 mg, cream

Imprinted with

LAMICTAL 150

200 mg, blue

Imprinted with

LAMICTAL 200

LAMICTAL (lamotrigine) tablets for oral suspension

2 mg, white

Imprinted with

LTG 2

5 mg, white

Imprinted with

GX CL2

25 mg, white

Imprinted with

GX CL5

LAMICTAL ODT (lamotrigine) orally disintegrating tablets

25 mg, white to off-white

Imprinted with

LMT on one side,

25 on the other

50 mg, white to off-white

Imprinted with

LMT on one side,

50 on the other

100 mg, white to off-white

Imprinted with

LAMICTAL on one side,

100 on the other

200 mg, white to off-white

Imprinted with

LAMICTAL on one side,

200 on the other

What is LAMICTAL?

- LAMICTAL is a prescription medicine used:
  - together with other medicines to treat certain types of seizures (partial-onset seizures, primary generalized tonic-clonic seizures, generalized seizures of Lennox-Gastaut syndrome) in people aged 2 years and older.
  - alone when changing from 1 other medicine used to treat partial-onset seizures in people aged 16 years and older.
  - for the long-term treatment of bipolar I disorder to lengthen the time between mood episodes in people who have been treated for mood episodes with other medicine.
- It is not known if LAMICTAL is safe or effective in people younger than 18 years with mood episodes such as bipolar disorder or depression.
- It is not known if LAMICTAL is safe or effective when used alone as the first treatment of seizures.
- It is not known if LAMICTAL is safe or effective for people with mood episodes who have not already been treated with other medicines.
- LAMICTAL should not be used for acute treatment of manic or mixed mood episodes.

Do not take LAMICTAL:

- if you have had an allergic reaction to lamotrigine or to any of the inactive ingredients in LAMICTAL. See the end of this leaflet for a complete list of ingredients in LAMICTAL.

Before taking LAMICTAL, tell your healthcare provider about all of your health conditions, including if you:

- have had a rash or allergic reaction to another antiseizure medicine.
- are of Asian origin, have had HLA testing before, and know you are carrying the genetic variant, HLA B*1502.
- have or have had depression, mood problems, or suicidal thoughts or behavior.
- have a history of heart problems or irregular heart beats or any of your family members have any heart problem, including genetic abnormalities.
- have had aseptic meningitis after taking LAMICTAL or LAMICTAL XR (lamotrigine).
- are taking estrogen-containing products, including oral contraceptives (birth control pills) or other female hormonal medicines (such as hormone replacement therapy). Do not start or stop taking birth control pills or other female hormonal medicine until you have talked with your healthcare provider. Tell your healthcare provider if you have any changes in your menstrual pattern such as breakthrough bleeding. Stopping these medicines while you are taking LAMICTAL may cause side effects (such as dizziness, lack of coordination, or double vision). Starting these medicines may lessen how well LAMICTAL works.
- are pregnant or plan to become pregnant. It is not known if LAMICTAL may harm your unborn baby. If you become pregnant while taking LAMICTAL, talk to your healthcare provider about registering with the North American Antiepileptic Drug Pregnancy Registry. You can enroll in this registry by calling 1-888-233-2334. The purpose of this registry is to collect information about the safety of antiepileptic drugs during pregnancy.
- are breastfeeding. LAMICTAL passes into breast milk and may cause side effects in a breastfed baby. If you breastfeed while taking LAMICTAL, watch your baby closely for trouble breathing, episodes of temporarily stopping breathing, sleepiness, or poor sucking. Call your baby’s healthcare provider right away if you see any of these problems. Talk to your healthcare provider about the best way to feed your baby if you take LAMICTAL.

Tell your healthcare provider about all the medicines you take, including prescription and over-the-counter medicines, vitamins, and herbal supplements. LAMICTAL and certain other medicines may interact with each other. This may cause serious side effects.

Know the medicines you take. Keep a list of them to show your healthcare provider and pharmacist when you get a new medicine.

How should I take LAMICTAL?

- Take LAMICTAL exactly as prescribed.
- Your healthcare provider may change your dose. Do not change your dose without talking to your healthcare provider.
- Do not stop taking LAMICTAL without talking to your healthcare provider. Stopping LAMICTAL suddenly may cause serious problems. For example, if you have epilepsy and you stop taking LAMICTAL suddenly, you may have seizures that do not stop. Talk with your healthcare provider about how to stop LAMICTAL slowly.
- If you miss a dose of LAMICTAL, take it as soon as you remember. If it is almost time for your next dose, just skip the missed dose. Take the next dose at your regular time. Do not take 2 doses at the same time.
- If you take too much LAMICTAL, call your healthcare provider or your local Poison Control Center or go to the nearest hospital emergency room right away.
- You may not feel the full effect of LAMICTAL for several weeks.
- If you have epilepsy, tell your healthcare provider if your seizures get worse or if you have any new types of seizures.
- Swallow LAMICTAL Tablets whole.
- If you have trouble swallowing LAMICTAL Tablets, tell your healthcare provider because there may be another form of LAMICTAL you can take.
- LAMICTAL ODT should be placed on the tongue and moved around the mouth. The tablet will rapidly disintegrate, can be swallowed with or without water, and can be taken with or without food.
- LAMICTAL tablets for oral suspension may be swallowed whole, chewed, or mixed in water or fruit juice mixed with water. If the tablets are chewed, drink a small amount of water or fruit juice mixed with water to help in swallowing. To break up LAMICTAL tablets for oral suspension, add the tablets to a small amount of liquid (1 teaspoon, or enough to cover the medicine) in a glass or spoon. Wait at least 1 minute or until the tablets are completely broken up, mix the solution together, and take the whole amount right away.
- If you receive LAMICTAL in a blister pack, examine the blister pack before use. Do not use if blisters are torn, broken, or missing.

What should I avoid while taking LAMICTAL?

Do not drive, operate machinery, or do other dangerous activities until you know how LAMICTAL affects you.

What are the possible side effects of LAMICTAL?

LAMICTAL can cause serious side effects.

See “What is the most important information I should know about LAMICTAL?”

Common side effects of LAMICTAL include:

- dizziness
- tremor
- headache
- rash
- blurred or double vision
- fever
- lack of coordination
- abdominal pain
- infections, including seasonal flu

- sleepiness
- back pain
- nausea, vomiting
- diarrhea
- tiredness
- insomnia
- dry mouth
- stuffy nose
- sore throat

These are not all the possible side effects of LAMICTAL.

Call your doctor for medical advice about side effects. You may report side effects to FDA at 1-800-FDA-1088.

How should I store LAMICTAL?

- Store LAMICTAL at room temperature between 68°F and 77°F (20°C and 25°C).

Keep LAMICTAL and all medicines out of the reach of children.

General information about the safe and effective use of LAMICTAL.

Medicines are sometimes prescribed for purposes other than those listed in a Medication Guide. Do not use LAMICTAL for a condition for which it was not prescribed. Do not give LAMICTAL to other people, even if they have the same symptoms that you have. It may harm them.

If you take a urine drug screening test, LAMICTAL may make the test result positive for another drug. If you require a urine drug screening test, tell the healthcare professional administering the test that you are taking LAMICTAL.

You can ask your healthcare provider or pharmacist for information about LAMICTAL that is written for health professionals.

What are the ingredients in LAMICTAL?

LAMICTAL tablets

Active ingredient: lamotrigine.

Inactive ingredients: lactose; magnesium stearate, microcrystalline cellulose, povidone, sodium starch glycolate, FD&C Yellow No. 6 Lake (100-mg tablet only), ferric oxide, yellow (150-mg tablet only), and FD&C Blue No. 2 Lake (200-mg tablet only).

LAMICTAL tablets for oral suspension

Active ingredient: lamotrigine.

Inactive ingredients: blackcurrant flavor, calcium carbonate, low-substituted hydroxypropylcellulose, magnesium aluminum silicate, magnesium stearate, povidone, saccharin sodium, and sodium starch glycolate.

LAMICTAL ODT orally disintegrating tablets

Active ingredient: lamotrigine.

Inactive ingredients: artificial cherry flavor, crospovidone, ethylcellulose, magnesium stearate, mannitol, polyethylene, and sucralose.

For more information about LAMICTAL, call 1-888-825-5249.

LAMICTAL and LAMICTAL ODT are trademarks owned by or licensed to the GSK group of companies. The other brands listed are trademarks owned by or licensed to their respective owners and are not owned by or licensed to the GSK group of companies. The makers of these brands are not affiliated with and do not endorse the GSK group of companies or its products.

Distributed by GlaxoSmithKline, Durham, NC 27701

©2025 GSK group of companies or its licensor.

LMT:21MG

This Medication Guide has been approved by the U.S. Food and Drug Administration Revised: October 2025

PACKAGE LABEL

PRINCIPAL DISPLAY PANEL

NDC 0173-0642-55

LAMICTAL

(LAMOTRIGINE)

TABLETS

100 mg

GSK

CAUTION: Verify Product Dispensed

100 Tablets

Dispense the accompanying Medication Guide to each patient.

Each scored tablet contains 100 mg of lamotrigine.

See Prescribing Information for dosage information.

Store at 25oC (77oF); excursions 15 to 30oC (59 to 86oF) [see USP Controlled Room Temperature] in a dry place and protect from light.

Do not accept if safety seal under cap is missing or broken.

Dispense in a tight, light-resistant container as defined in the USP.

Distributed by

GlaxoSmithKline

Durham, NC 27701

Made in India

Trademark owned or licensed by GSK.

©2023 GSK group of companies or its licensor.

Rx only

A087386 (62000000087386) Rev. 4/23

PACKAGE LABEL

PRINCIPAL DISPLAY PANEL

NDC 0173-0643-60

LAMICTAL

(LAMOTRIGINE)

TABLETS

150 mg

GSK

CAUTION: Verify Product Dispensed

60 Tablets

Dispense the accompanying Medication Guide to each patient.

Each scored tablet contains 150 mg of lamotrigine.

See Prescribing Information for dosage information.

Store at 25oC (77oF); excursions 15-30oC (59-86oF) [see USP Controlled Room Temperature] in a dry place and protect from light.

Do not accept if safety seal under cap is missing or broken.

Dispense in a tight, light-resistant container as defined in the USP.

Distributed by

GlaxoSmithKline

Durham, NC 27701

Made in India

Trademark owned or licensed by GSK.

©2023 GSK group of companies or its licensor.

Rx only

A086833 (62000000086833) Rev. 4/23

PACKAGE LABEL

PRINCIPAL DISPLAY PANEL

NDC 0173-0644-60

LAMICTAL

(LAMOTRIGINE)

TABLETS

200 mg

GSK

CAUTION: Verify Product Dispensed

60 Tablets

Dispense the accompanying Medication Guide to each patient.

Each scored tablet contains 200 mg of lamotrigine.

See Prescribing Information for dosage information.

Store at 25oC (77oF); excursions 15 to 30oC (59 to 86oF) [see USP Controlled Room Temperature] in a dry place and protect from light.

Do not accept if safety seal under cap is missing or broken.

Dispense in a tight, light-resistant container as defined in the USP.

Distributed by

GlaxoSmithKline

Durham, NC 27701

Made in India

Trademark owned or licensed by GSK.

©2023 GSK group of companies or its licensor.

Rx only

A0868332 (62000000086832) Rev. 4/23

PACKAGE LABEL

PRINCIPAL DISPLAY PANEL

NDC 0173-0633-10

LAMICTAL

(LAMOTRIGINE)

TABLETS

GSK

RX ONLY

For patients TAKING valproate*

*See prescribing information for other drugs that may affect dosing of LAMICTAL.

STARTER KIT

Contains: 35 25-mg Tablets

Weeks | Tablets per day
1&2 | Take 1 (25 mg) tablet every OTHER day
3&4 | Take 1 (25 mg) tablets once a day
5 | Take 2 (25 mg) tablet once a day

Please check with your physician about proper maintenance dose before week 5.

Dispense the enclosed Medication Guide to each patient.

Each LAMICTAL 25 tablet contains 25 mg of lamotrigine

CAUTION: Verify Product Dispensed

Do not use if blisters are torn, broken, or missing.

Made in India

©2023 GSK group of companies or its licensor

546716-02 Rev.6/23

PACKAGE LABEL

PRINCIPAL DISPLAY PANEL

NDC 0173-0817-28

LAMICTAL

(LAMOTRIGINE)

TABLETS

GSK

RX ONLY

For patients TAKING carbamazepine, phenytoin, phenobarbital, or primidone and NOT TAKING valproate*

*See prescribing information for other drugs that may affect dosing of LAMICTAL.

STARTER KIT

Contains: 84 25-mg Tablets

14 100-mg Tablets

Weeks | Tablets per day
1&2 | Take 2 (25 mg) tablets once a day
3&4 | Take 2 (25 mg) tablets twice a day
5 | Take 1 (100 mg) tablet twice a day

Please check with your physician about proper maintenance dose before week 5.

Dispense the enclosed Medication Guide to each patient.

Each LAMICTAL 25 tablet contains 25 mg of lamotrigine

Each LAMICTAL 100 tablet contains 100 mg of lamotrigine

CAUTION: Verify Product Dispensed

Do not use if blisters are torn, broken, or missing.

Made in India

©2023 GSK group of companies or its licensor

546714-02 Rev. 6/23

PACKAGE LABEL

PRINCIPAL DISPLAY PANEL

NDC 0173-0594-02

LAMICTAL

(LAMOTRIGINE)

TABLETS

GSK

RX ONLY

For patients NOT TAKING carbamazepine, phenytoin, phenobarbital, primidone, or valproate*

*See prescribing information for other drugs that may affect dosing of LAMICTAL.

STARTER KIT

Contains: 42 25-mg Tablets

7 100-mg Tablets

Weeks | Tablets per day
1&2 | Take 1 (25 mg) tablet once a day
3&4 | Take 2 (25 mg) tablets once a day
5 | Take 1 (100 mg) tablet once a day

Please check with your physician about proper maintenance dose before week 5.

Dispense the enclosed Medication Guide to each patient.

Each LAMICTAL 25 tablet contains 25 mg of lamotrigine

Each LAMICTAL 100 tablet contains 100 mg of lamotrigine

CAUTION: Verify Product Dispensed

Do not use if blisters are torn, broken, or missing.

Made in India

©2023 the GSK group of companies

546718-02 Rev. 6/23

PACKAGE LABEL

PRINCIPAL DISPLAY PANEL

NDC 0173-0699-00

LAMICTAL

(LAMOTRIGINE)

TABLETS FOR ORAL SUSPENSION

2 mg

GSK

CAUTION: Verify Product Dispensed

30 Tablets

Dispense the accompanying Medication Guide to each patient.

Each tablet contains 2 mg of lamotrigine. Tablets may be swallowed whole, chewed, or dispersed in water or diluted fruit juice.

See Prescribing Information for dosage information.

Store at 25°C (77°F); excursions permitted to 15°C to 30°C (59°F to 86°F) [see USP Controlled Room Temperature] in a dry place.

Do not accept if membrane seal under cap is missing or broken.

Dispense in a tight, light-resistant container as defined in the USP.

Distributed by

GlaxoSmithKline

Durham, NC 27701

Made in India

Trademark owned or licensed by GSK.

©2023 GSK group of companies or its licensor.

Rx only

Rev. 2/23
A086205 (62000000086205)

PACKAGE LABEL

PRINCIPAL DISPLAY PANEL

NDC 0173-0526-00

LAMICTAL

(LAMOTRIGINE)

TABLETS FOR ORAL SUSPENSION

5 mg

GSK

CAUTION: Verify Product Dispensed

100 Tablets

Dispense the accompanying Medication Guide to each patient.

Each tablet contains 5 mg of lamotrigine. Tablets may be swallowed whole, chewed, or dispersed in water or diluted fruit juice.

See Prescribing Information for dosage information.

Store at 25°C (77°F); excursions permitted to 15°C to 30°C (59°F to 86°F) [see USP Controlled Room Temperature] in a dry place.

Do not accept if membrane seal under cap is missing or broken.

Dispense in a tight, light-resistant container as defined in the USP.

Distributed by

GlaxoSmithKline

Durham, NC 27701

Made in India

Trademark owned or licensed by GSK.

©2023 GSK group of companies or its licensor.

Rx only

Rev. 2/23
A086204 (62000000086204)

PACKAGE LABEL

PRINCIPAL DISPLAY PANEL

NDC 0173-0527-00

LAMICTAL

(LAMOTRIGINE)

TABLETS FOR ORAL SUSPENSION

25 mg

GSK

CAUTION: Verify Product Dispensed

100 Tablets

Dispense the accompanying Medication Guide to each patient.

Each tablet contains 25 mg of lamotrigine. Tablets may be swallowed whole, chewed, or dispersed in water or diluted fruit juice.

See Prescribing Information for dosage information.

Store at 25°C (77°F); excursions permitted to 15°C to 30°C (59°F to 86°F) [see USP Controlled Room Temperature] in a dry place.

Do not accept if membrane seal under cap is missing or broken.

Dispense in a tight, light-resistant container as defined in the USP.

Distributed by

GlaxoSmithKline

Durham, NC 27701

Made in India

Trademark owned or licensed by GSK.

©2023 GSK group of companies or its licensor.

Rx only

Rev. 2/23
A086207 (62000000086207)

PACKAGE LABEL

PRINCIPAL DISPLAY PANEL

NDC 0173-0772-02

LAMICTAL ODT

(LAMOTRIGINE)

ORALLY DISINTEGRATING TABLETS

25 mg

Rx only

Maintenance Pack

GSK

25 mg

30 Tablets

This Maintenance Pack is intended for patients already taking LAMICTAL.

NOT for initial titration.

Dispense the accompanying Medication Guide to each patient.

CAUTION: Verify Product Dispensed

Made in India

©2023 GSK group of companies or its licensor

547954-02 Rev. 6/23

PACKAGE LABEL

PRINCIPAL DISPLAY PANEL

NDC 0173-0774-02

LAMICTAL ODT

(LAMOTRIGINE)

ORALLY DISINTEGRATING TABLETS

50 mg

Rx only

Maintenance Pack

GSK

50 mg

30 Tablets

This Maintenance Pack is intended for patients already taking LAMICTAL

NOT for initial titration.

Dispense the accompanying Medication Guide to each patient.

CAUTION: Verify Product Dispensed

Made in India

©2023 GSK group of companies or its licensor

547955-02 Rev. 6/23

PACKAGE LABEL

PRINCIPAL DISPLAY PANEL

NDC 0173-0776-02

LAMICTAL ODT

(LAMOTRIGINE)

ORALLY DISINTEGRATING TABLETS

100 mg

Rx only

Maintenance Pack

GSK

100 mg

30 Tablets

This Maintenance Pack is intended for patients already taking LAMICTAL.

NOT for initial titration.

Dispense the accompanying Medication Guide to each patient.

CAUTION: Verify Product Dispensed

Made in India

©2023 GSK group of companies or its licensor

547956-02 Rev. 6/23

PACKAGE LABEL

PRINCIPAL DISPLAY PANEL

NDC 0173-0777-02

LAMICTAL ODT

(LAMOTRIGINE)

ORALLY DISINTEGRATING TABLETS

200 mg

Rx only

Maintenance Pack

GSK

200 mg

30 Tablets

This Maintenance Pack is intended for patients already taking LAMICTAL.

NOT for initial titration.

Dispense the accompanying Medication Guide to each patient.

CAUTION: Verify Product Dispensed

Made in India

©2023 GSK group of companies or its licensor

547957-02 Rev. 6/23

PACKAGE LABEL

PRINCIPAL DISPLAY PANEL

NDC 0173-0779-00

LAMICTAL ODT

(LAMOTRIGINE)

ORALLY DISINTEGRATING TABLETS

RX only

Patient Titration Kit

For patients TAKING valproate*

*See prescribing information for other drugs that may affect dosing of LAMICTAL ODT.

KIT CONTAINS:

21 | 25 mg Tablets
7 | 50 mg Tablets

WEEKS | TABLETS PER DAY
1&2 | Take 1 (25 mg) tablet every OTHER day
3&4 | Take 1 (25 mg) tablet ONCE a day
5 | Take 1 (50 mg) tablet ONCE a day

Dispense the accompanying Medication Guide to each patient.

CAUTION: Verify Product Dispensed

Do not use if blisters are torn, broken, or missing.

©2023 GSK group of companies or its licensor

Rev. 6/23

548811-02

PACKAGE LABEL

PRINCIPAL DISPLAY PANEL

NDC 0173-0780-00

LAMICTAL ODT

(LAMOTRIGINE)

ORALLY DISINTEGRATING TABLETS

RX only

Patient Titration Kit

GSK

For patients TAKING carbamazepine, phenytoin, phenobarbital, or primidone, and NOT TAKING valproate*

*See prescribing information for other drugs that may affect dosing of LAMICTAL ODT.

KIT CONTAINS:

42 | 50 mg Tablets
14 | 100 mg Tablets

WEEKS | TABLETS PER DAY
1&2 | Take 1 (50 mg) tablet ONCE a day
3&4 | Take 1 (50 mg) tablet TWICE a day
5 | Take 1 (100 mg) tablet TWICE a day

Dispense the accompanying Medication Guide to each patient.

CAUTION: Verify Product Dispensed

Do not use if blisters are torn, broken, or missing.

©2023 GSK group of companies or its licensor

Rev. 6/23

548810-02

PACKAGE LABEL

PRINCIPAL DISPLAY PANEL

NDC 0173-0778-00

LAMICTAL ODT

(LAMOTRIGINE)

ORALLY DISINTEGRATING TABLETS

RX ONLY

Patient Titration Kit

GSK

For patients NOT TAKING carbamazepine, phenytoin, phenobarbital, primidone, or valproate*

*See prescribing information for other drugs that may affect dosing of LAMICTAL ODT.

KIT CONTAINS:

14 | 25 mg Tablets
14 | 50 mg Tablets
7 | 100 mg Tablets

WEEKS | TABLETS PER DAY
1&2 | Take 1 (25 mg) tablet ONCE a day
3&4 | Take 1 (50 mg) tablet ONCE a day
5 | Take 1 (100 mg) tablet ONCE a day

Dispense the accompanying Medication Guide to each patient.

CAUTION: Verify Product Dispensed

Do not use if blisters are torn, broken, or missing.

©2023 GSK group of companies or its licensor

Rev. 6/23

548809-02